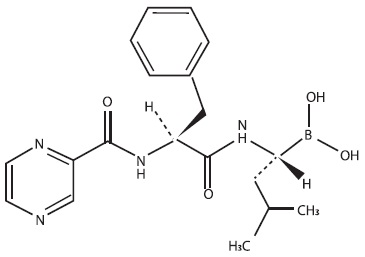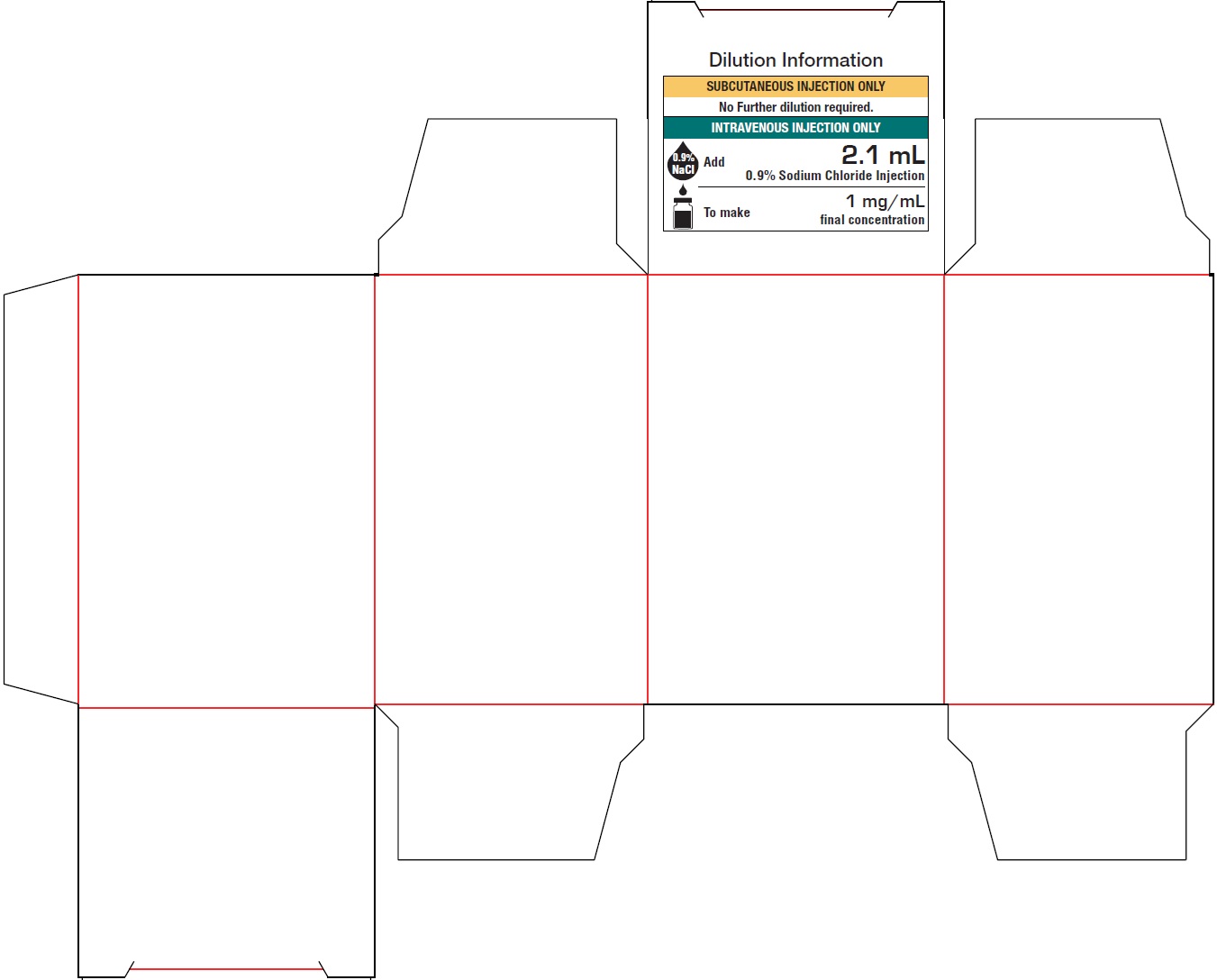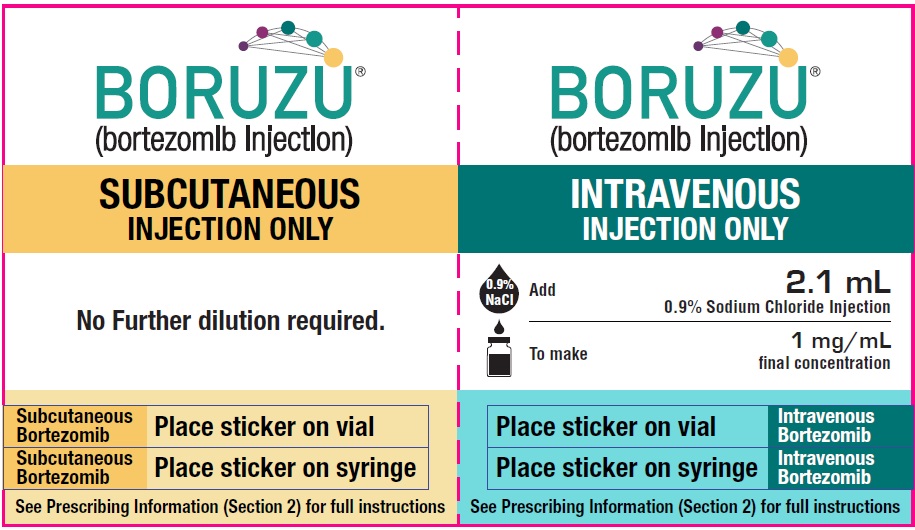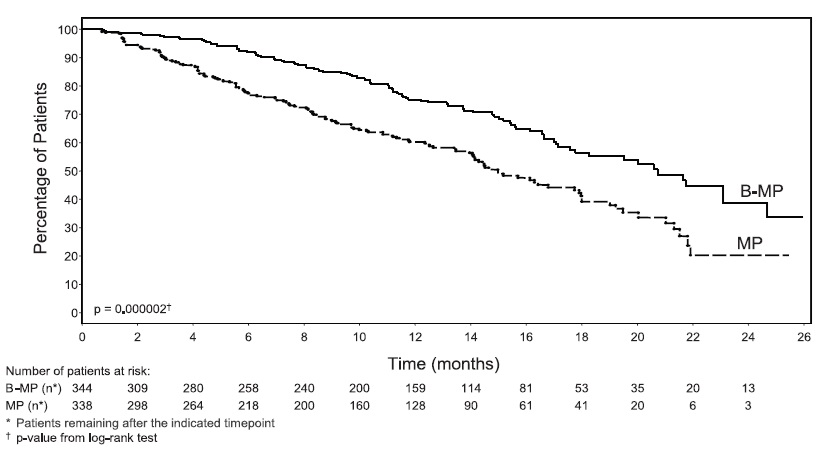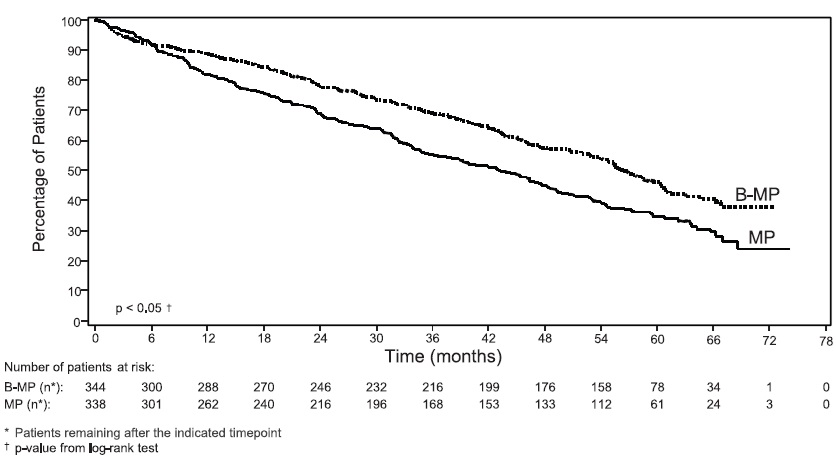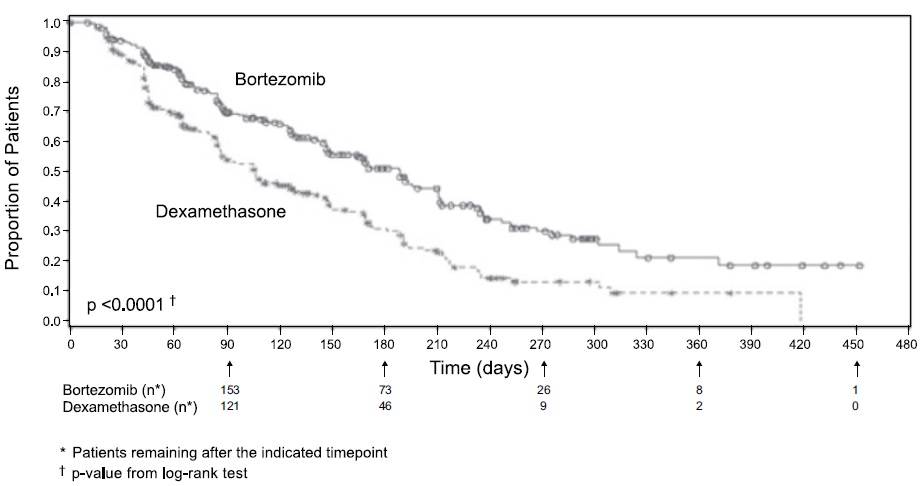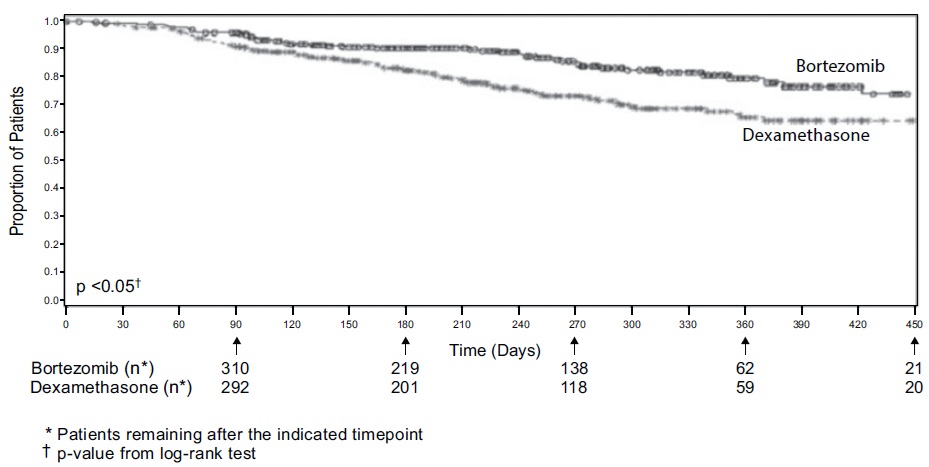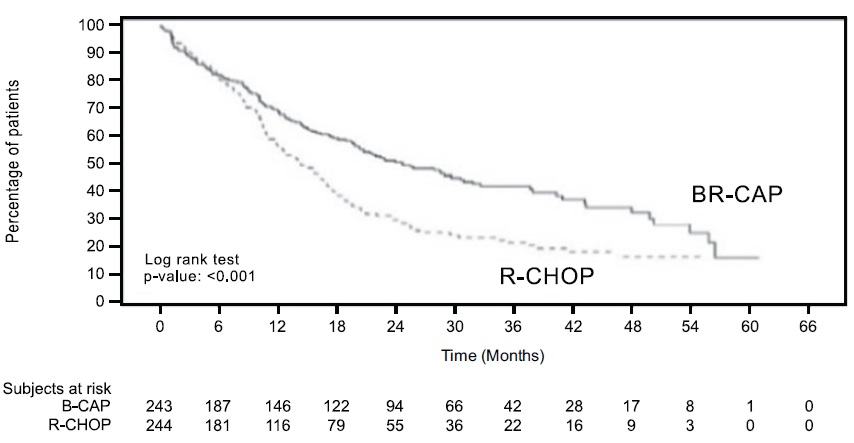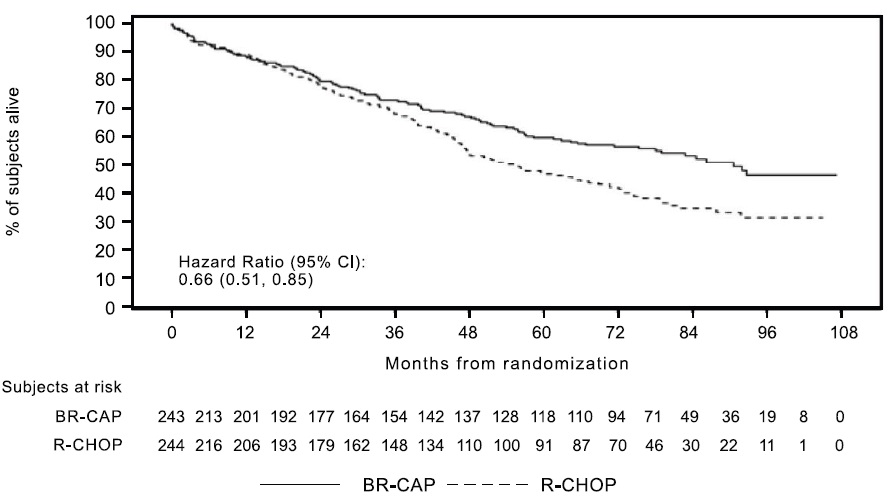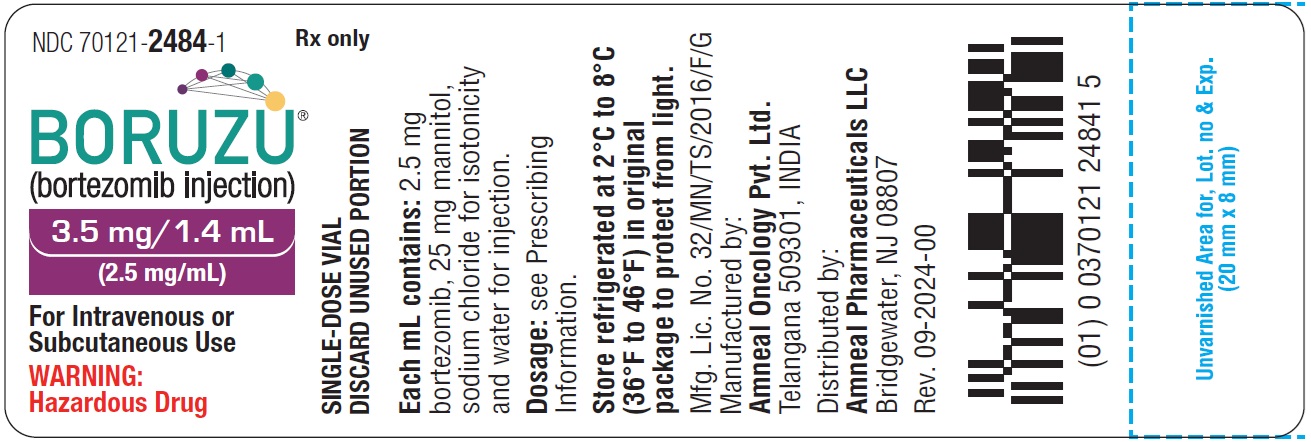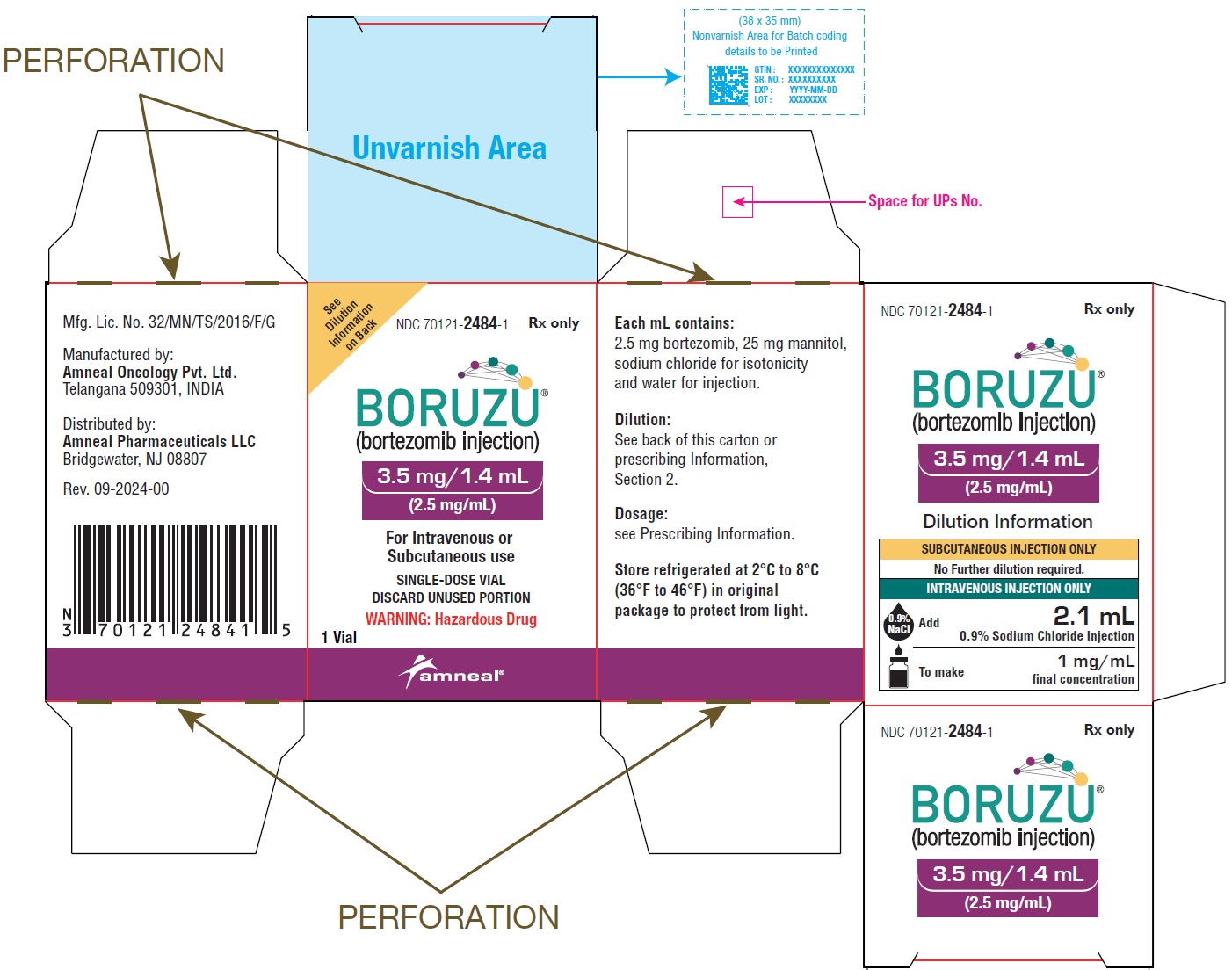 DRUG LABEL: BORUZU
NDC: 70121-2484 | Form: INJECTION
Manufacturer: Amneal Pharmaceuticals LLC
Category: prescription | Type: HUMAN PRESCRIPTION DRUG LABEL
Date: 20250705

ACTIVE INGREDIENTS: BORTEZOMIB 3.5 mg/1.4 mL

HIGHLIGHTS OF PRESCRIBING INFORMATION

These highlights do not include all the information needed to use BORUZU safely and effectively. See full prescribing information for BORUZU.
BORUZU® (bortezomib injection), for subcutaneous or intravenous use
Initial U.S. Approval: 2003

1 INDICATIONS AND USAGE

BORUZU is a proteasome inhibitor indicated for:

- treatment of adult patients with multiple myeloma (1.1)
- treatment of adult patients with mantle cell lymphoma (1.2)

2 DOSAGE AND ADMINISTRATION

- For subcutaneous or intravenous use only. Each route of administration has a different final concentration. Exercise caution when calculating the volume to be administered. (2.1, 2.10)
- The recommended starting dose of BORUZU is 1.3 mg/m^2 administered either as a 3 to 5 second bolus intravenous injection or subcutaneous injection. (2.2, 2.4, 2.6)
- Retreatment for Multiple Myeloma: May retreat starting at the last tolerated dose. (2.6)
- Hepatic Impairment: Use a lower starting dose for patients with moderate or severe hepatic impairment. (2.8)
- Dose must be individualized to prevent overdose. (2.10)
- See Full Prescribing Information for preparation and administration instructions. (2.10)

3 DOSAGE FORMS AND STRENGTHS

Injection: 3.5 mg/1.4 mL (2.5 mg/mL) in a single-dose vial. (3)

4 CONTRAINDICATIONS

- Patients with hypersensitivity (not including local reactions) to bortezomib, boron, or mannitol, including anaphylactic reactions. (4)
- Contraindicated for intrathecal administration. (4)

5 WARNINGS AND PRECAUTIONS

- Peripheral Neuropathy: Manage with dose modification or discontinuation. (2.7) Patients with pre-existing severe neuropathy should be treated with BORUZU only after careful risk-benefit assessment. (2.7, 5.1)
- Hypotension: Use caution when treating patients taking antihypertensives, with a history of syncope, or with dehydration. (5.2)
- Cardiac Toxicity: Worsening of and development of cardiac failure has occurred. Closely monitor patients with existing heart disease or risk factors for heart disease. (5.3)
- Pulmonary Toxicity: Acute respiratory syndromes have occurred. Monitor closely for new or worsening symptoms and consider interrupting BORUZU therapy. (5.4)
- Posterior Reversible Encephalopathy Syndrome: Consider MRI imaging for onset of visual or neurological symptoms; discontinue BORUZU if suspected. (5.5)
- Gastrointestinal Toxicity: Nausea, diarrhea, constipation, and vomiting may require use of antiemetic and antidiarrheal medications or fluid replacement. (5.6)
- Thrombocytopenia and Neutropenia: Monitor complete blood counts regularly throughout treatment. (5.7)
- Tumor Lysis Syndrome: Closely monitor patients with high tumor burden. (5.8)
- Hepatic Toxicity: Monitor hepatic enzymes during treatment. Interrupt BORUZU therapy to assess reversibility. (5.9)
- Thrombotic Microangiopathy: Monitor for signs and symptoms. Discontinue BORUZU if suspected. (5.10)
- Embryo-Fetal Toxicity: BORUZU can cause fetal harm. Advise females of reproductive potential and males with female partners of reproductive potential of the potential risk to a fetus and to use effective contraception. (5.11)

6 ADVERSE REACTIONS

Most commonly reported adverse reactions (≥ 20%) in clinical studies include nausea, diarrhea, thrombocytopenia, neutropenia, peripheral neuropathy, fatigue, neuralgia, anemia, leukopenia, constipation, vomiting, lymphopenia, rash, pyrexia, and anorexia. (6.1)

To report SUSPECTED ADVERSE REACTIONS, contact Amneal Pharmaceuticals LLC at 1-877-835-5472 or FDA at 1-800-FDA-1088 or www.fda.gov/medwatch.

7 DRUG INTERACTIONS

- Strong CYP3A4 Inhibitors: Closely monitor patients with concomitant use. (7.1)
- Strong CYP3A4 Inducers: Avoid concomitant use. (7.3)

8 USE IN SPECIFIC POPULATIONS

Patients with diabetes may require close monitoring of blood glucose and adjustment of antidiabetic medication. (8.8)

FULL PRESCRIBING INFORMATION

1 INDICATIONS AND USAGE

1.1 Multiple Myeloma

BORUZU is indicated for the treatment of adult patients with multiple myeloma.

1.2 Mantle Cell Lymphoma

BORUZU is indicated for the treatment of adult patients with mantle cell lymphoma.

2 DOSAGE AND ADMINISTRATION

2.1 Important Dosing Guidelines

BORUZU is for intravenous or subcutaneous use only. Do not administer BORUZU by any other route.

Because each route of administration has a different final concentration, use caution when calculating the volume to be administered.

The recommended starting dose of BORUZU is 1.3 mg/m^2. BORUZU is administered intravenously at a concentration of 1 mg/mL, or subcutaneously at a concentration of 2.5 mg/mL [see Dosage and Administration (2.10)].

BORUZU retreatment may be considered for patients with multiple myeloma who had previously responded to treatment with BORUZU and who have relapsed at least six months after completing prior BORUZU treatment. Treatment may be started at the last tolerated dose [see Dosage and Administration (2.6)].

When administered intravenously, administer BORUZU as a 3 to 5 second bolus intravenous injection.

2.2 Dosage in Previously Untreated Multiple Myeloma

BORUZU is administered in combination with oral melphalan and oral prednisone for 9, six week treatment cycles as shown in Table 1. In Cycles 1 to 4, BORUZU is administered twice weekly (Days 1, 4, 8, 11, 22, 25, 29 and 32). In Cycles 5 to 9, BORUZU is administered once weekly (Days 1, 8, 22 and 29). At least 72 hours should elapse between consecutive doses of BORUZU.

Table 1: Dosage Regimen for Patients with Previously Untreated Multiple Myeloma

Twice Weekly BORUZU (Cycles 1 to 4)
Week | 1 |  |  |  | 2 |  | 3 | 4 |  | 5 |  | 6
BORUZU; (1.3 mg/m^2) | Day; 1 | -- | -- | Day 4 | Day 8 | Day 11 | rest period | Day 22 | Day 25 | Day 29 | Day 32 | rest period
Melphalan; (9 mg/m^2) Prednisone; (60 mg/m^2) | Day 1 | Day 2 | Day 3 | Day 4 | -- | -- | rest period | -- | -- | -- | -- | rest period
Once Weekly BORUZU (Cycles 5 to 9 when used in combination with Melphalan and Prednisone)
Week | 1 |  |  |  | 2 |  | 3 | 4 |  | 5 |  | 6
BORUZU; (1.3 mg/m^2) | Day 1 | -- | -- |  | Day 8 |  | rest period | Day 22 |  | Day 29 |  | rest period
Melphalan (9 mg/m^2) Prednisone (60 mg/m^2) | Day 1 | Day 2 | Day 3 | Day 4 | -- | -- | rest period | -- | -- | -- | -- | rest period

2.3 Dosage Modification Guidelines for BORUZU When Given in Combination with Melphalan and Prednisone

Prior to initiating any cycle of therapy with BORUZU in combination with melphalan and prednisone:

- Platelet count should be at least 70 x 10^9/L and the absolute neutrophil count (ANC) should be at least 1 x 10^9/L
- Nonhematological toxicities should have resolved to Grade 1 or baseline

Table 2: Dosage Modifications During Cycles of Combination BORUZU, Melphalan and Prednisone Therapy

Toxicity | Dose Modification or Delay
Hematological toxicity during a cycle:; If prolonged Grade 4 neutropenia or thrombocytopenia, or thrombocytopenia with bleeding is observed in the previous cycle | Consider reduction of the melphalan dose by 25% in the next cycle
If platelet count is not above 30 × 10^9/L or ANC is not above 0.75 x 10^9/L on a BORUZU dosing day (other than Day 1) | Withhold BORUZU dose
If several BORUZU doses in consecutive cycles are withheld due to toxicity | Reduce BORUZU dose by one dose level (from 1.3 mg/m^2 to 1 mg/m^2, or from 1 mg/m^2 to 0.7 mg/m^2)
Grade 3 or higher nonhematological toxicities | Withhold BORUZU therapy until symptoms of toxicity have resolved to Grade 1 or baseline. Then, BORUZU may be reinitiated with one dose level reduction (from 1.3 mg/m^2 to 1 mg/m^2, or from 1 mg/m^2 to 0.7 mg/m^2). For BORUZU-related neuropathic pain and/or peripheral neuropathy, hold or modify BORUZU as outlined in Table 5.

For information concerning melphalan and prednisone, see manufacturer's prescribing information.

Dose modifications guidelines for peripheral neuropathy are provided [see Dosage and Administration (2.7)].

2.4 Dosage in Previously Untreated Mantle Cell Lymphoma

BORUZU (1.3 mg/m^2) is administered intravenously in combination with intravenous rituximab, cyclophosphamide, doxorubicin and oral prednisone (BR-CAP) for 6, three week treatment cycles as shown in Table 3. BORUZU is administered first followed by rituximab. BORUZU is administered twice weekly for two weeks (Days 1, 4, 8, and 11) followed by a ten day rest period on Days 12 to 21. For patients with a response first documented at Cycle 6, two additional BR-CAP cycles are recommended. At least 72 hours should elapse between consecutive doses of BORUZU.

Table 3: Dosage Regimen for Patients with Previously Untreated Mantle Cell Lymphoma

Twice Weekly BORUZU (6, Three Week Cycles)*
Week | 1 |  |  |  |  | 2 |  | 3
BORUZU (1.3 mg/m^2) | Day 1 | - | - | Day 4 | - | Day 8 | Day 11 | rest period
Rituximab (375 mg/m^2); Cyclophosphamide (750 mg/m^2); Doxorubicin (50 mg/m^2) | Day 1 | - | - |  |  | - | - | rest period
Prednisone (100 mg/m^2) | Day 1 | Day 2 | Day 3 | Day 4 | Day 5 | - | - | rest period
* Dosing may continue for two more cycles (for a total of eight cycles) if response is first seen at Cycle 6.

2.5 Dosage Modification Guidelines for BORUZU When Given in Combination with Rituximab, Cyclophosphamide, Doxorubicin and Prednisone

Prior to the first day of each cycle (other than Cycle 1):

- Platelet count should be at least 100 x 10^9/L and absolute neutrophil count (ANC) should be at least 1.5 x 10^9/L
- Hemoglobin should be at least 8 g/dL (at least 4.96 mmol/L)
- Nonhematologic toxicity should have recovered to Grade 1 or baseline

Interrupt BORUZU treatment at the onset of any Grade 3 hematologic or nonhematological toxicities, excluding neuropathy [see Table 5, Warnings and Precautions (5)]. For dose adjustments, see Table 4 below.

Table 4: Dosage Modifications on Days 4, 8, and 11 During Cycles of Combination BORUZU, Rituximab, Cyclophosphamide, Doxorubicin and Prednisone Therapy

Toxicity | Dosage Modification or Delay
Hematological Toxicity
Grade 3 or higher neutropenia, or a platelet count not at or above 25 x 10^9/L | Withhold BORUZU therapy for up to 2 weeks until the patient has an ANC at or above 0.75 x 10^9/L and a platelet count at or above 25 x 10^9/L.; - If, after BORUZU has been withheld, the toxicity does not resolve, discontinue BORUZU. - If toxicity resolves such that the patient has an ANC at or above 0.75 x 10^9/L and a platelet count at or above 25 x 10^9/L,; BORUZU dose should be reduced by 1 dose level (from 1.3 mg/m^2to 1 mg/m^2, or from 1 mg/m^2to 0.7 mg/m^2).
Grade 3 or higher nonhematological toxicities | Withhold BORUZU therapy until symptoms of the toxicity have resolved to Grade 2 or better. Then, BORUZU may be reinitiated with one dose level reduction (from 1.3 mg/m^2 to 1 mg/m^2, or from 1 mg/m^2 to 0.7 mg/m^2).; For BORUZU-related neuropathic pain and/or peripheral neuropathy, hold or modify BORUZU as outlined in Table 5.

For information concerning rituximab, cyclophosphamide, doxorubicin and prednisone, see manufacturer's prescribing information.

2.6 Dosage and Dose Modifications for Relapsed Multiple Myeloma and Relapsed Mantle Cell Lymphoma

Bortezomib (1.3 mg/m^2/dose) is administered twice weekly for two weeks (Days 1, 4, 8, and 11) followed by a ten day rest period (Days 12 to 21). For extended therapy of more than eight cycles, bortezomib may be administered on the standard schedule or, for relapsed multiple myeloma, on a maintenance schedule of once weekly for four weeks (Days 1, 8, 15, and 22) followed by a 13 day rest period (Days 23 to 35) [see Clinical Studies (14)]. At least 72 hours should elapse between consecutive doses of bortezomib.

Patients with multiple myeloma who have previously responded to treatment with bortezomib (either alone or in combination) and who have relapsed at least six months after their prior bortezomib therapy may be started on bortezomib at the last tolerated dose. Retreated patients are administered bortezomib twice weekly (Days 1, 4, 8, and 11) every three weeks for a maximum of eight cycles. At least 72 hours should elapse between consecutive doses of bortezomib. Bortezomib may be administered either as a single agent or in combination with dexamethasone [see Clinical Studies (14.1)].

BORUZU therapy should be withheld at the onset of any Grade 3 nonhematological or Grade 4 hematological toxicities excluding neuropathy as discussed below [see Warnings and Precautions (5)]. Once the symptoms of the toxicity have resolved, BORUZU therapy may be reinitiated at a 25% reduced dose (1.3 mg/m^2/dose reduced to 1 mg/m^2/dose; 1 mg/m^2/dose reduced to 0.7 mg/m^2/dose).

For dosage modifications guidelines for peripheral neuropathy see section 2.7.

2.7 Dosage Modifications for Peripheral Neuropathy

Starting BORUZU subcutaneously may be considered for patients with pre-existing or at high risk of peripheral neuropathy. Patients with pre-existing severe neuropathy should be treated with BORUZU only after careful risk-benefit assessment.

Patients experiencing new or worsening peripheral neuropathy during BORUZU therapy may require a decrease in the dose and/or a less dose-intense schedule.

For dose or schedule modification guidelines for patients who experience BORUZU-related neuropathic pain and/or peripheral neuropathy, see Table 5.

Table 5: Recommended Dosage Modification for BORUZU-Related Neuropathic Pain and/or Peripheral Sensory or Motor Neuropathy

Severity of Peripheral Neuropathy Signs and Symptoms* | Modification of Dose and Regimen
Grade 1 (asymptomatic; loss of deep tendon reflexes or paresthesia) without pain or loss of function | No action
Grade 1 with pain or Grade 2 (moderate symptoms; limiting instrumental Activities of Daily Living (ADL)†) | Reduce BORUZU to 1 mg/m^2
Grade 2 with pain or Grade 3 (severe symptoms; limiting self care ADL‡) | Withhold BORUZU therapy until toxicity resolves. When toxicity resolves reinitiate with a reduced dose of BORUZU at 0.7 mg/m^2 once per week.
Grade 4 (life-threatening consequences; urgent intervention indicated) | Discontinue BORUZU
* Grading based on NCI Common Terminology Criteria CTCAE v4.0
† Instrumental ADL: refers to preparing meals, shopping for groceries or clothes, using telephone, managing money, etc.
‡ Self care ADL: refers to bathing, dressing and undressing, feeding self, using the toilet, taking medications, and not bedridden

2.8 Dosage in Patients with Hepatic Impairment

Do not adjust the starting dose for patients with mild hepatic impairment.

Start patients with moderate or severe hepatic impairment at a reduced dose of 0.7 mg/m^2 per injection during the first cycle, and consider subsequent dose escalation to 1 mg/m^2 or further dose reduction to 0.5 mg/m^2 based on patient tolerance (see Table 6) [see Use in Specific Populations (8.7), Clinical Pharmacology (12.3)].

Table 6: Recommended Starting Dose Modification for BORUZU in Patients with Hepatic Impairment

 | Bilirubin Level | SGOT (AST) Levels | Modification of Starting Dose
Mild | Less than or equal to 1 × ULN | More than ULN | None
Mild | More than 1 × to 1.5 x ULN | Any | None
Moderate | More than 1.5 × to 3 × ULN | Any | Reduce BORUZU to 0.7 mg/m^2 in the first cycle. Consider dose escalation to 1 mg/m^2 or further dose reduction to 0.5 mg/m^2 in subsequent cycles based on patient tolerability.
Severe | More than 3 × ULN | Any | Reduce BORUZU to 0.7 mg/m^2 in the first cycle. Consider dose escalation to 1 mg/m^2 or further dose reduction to 0.5 mg/m^2 in subsequent cycles based on patient tolerability.
Abbreviations: SGOT = serum glutamic oxaloacetic transaminase; AST = aspartate aminotransferase; ULN = upper limit of the normal range.

2.9 Administration Precautions

The drug quantity contained in one vial may exceed the usual dose required. Use caution in calculating the dose to prevent overdose [see Dosage and Administration (2.10)].

When administered subcutaneously, sites for each injection (thigh or abdomen) should be rotated. New injections should be given at least one inch from an old site and never into areas where the site is tender, bruised, erythematous, or indurated.

If local injection site reactions occur following BORUZU administration subcutaneously, a less concentrated BORUZU (1 mg/mL instead of 2.5 mg/mL) may be administered subcutaneously [see Dosage and Administration (2.10)]. Alternatively, consider use of the

intravenous route of administration [see Dosage and Administration (2.10)].

BORUZU is a hazardous drug. Follow applicable special handling and disposal procedures.^1

2.10 Preparation for Intravenous and Subcutaneous Administration

Use proper aseptic technique.

Instructions for Intravenous Administration

Dilute each vial with 2.1 mL of 0.9% Sodium Chloride Injection only to obtain a final concentration of 1 mg/mL (see Table 7). The diluted solution should be clear and colorless.

Table 7: Dilution Volume and Final Concentration for Intravenous Administration

Route of Administration | Strength | Diluent (0.9% Sodium Chloride Injection) | Final BORUZU Concentration (mg/mL)
Intravenous | 3.5 mg/1.4 mL | 2.1 mL | 1 mg/mL

Instructions for Subcutaneous Administration

No dilution is required for subcutaneous route of administration.

The concentration of bortezomib for subcutaneous administration (2.5 mg/mL) is greater than the diluted concentration of bortezomib for intravenous administration (1 mg/mL). Use caution when calculating the volume to be administered because each route of administration has a different final concentration.

Stickers that indicate the route of administration are provided with each BORUZU vial. Place the sticker directly on the syringe of BORUZU once the required volume of BORUZU has been withdrawn from the vial to help to alert practitioners of the correct route of administration for BORUZU.

Parenteral drug products should be inspected visually for particulate matter and discoloration prior to administration whenever solution and container permit. If any discoloration or particulate matter is observed, the diluted product should not be used. Discard any unused portion.

Stability

BORUZU contains no antimicrobial preservative. The diluted product may be stored in the original vial and/or syringe at room temperature (20°C to 25°C [68°F to 77°F]) for up to 8 hours prior to use when exposed to normal indoor lighting.

3 DOSAGE FORMS AND STRENGTHS

Injection: supplied as a sterile clear to light yellow solution available as a 3.5 mg/1.4 mL (2.5 mg/mL) in a single-dose vial.

4 CONTRAINDICATIONS

BORUZU is contraindicated in patients with hypersensitivity (not including local reactions) to bortezomib, boron, or mannitol. Reactions have included anaphylactic reactions [see Adverse Reactions (6.1)].

BORUZU is contraindicated for intrathecal administration. Fatal events have occurred with intrathecal administration of BORUZU.

5 WARNINGS AND PRECAUTIONS

5.1 Peripheral Neuropathy

Bortezomib treatment causes a peripheral neuropathy that is predominantly sensory; however, cases of severe sensory and motor peripheral neuropathy have been reported. Patients with pre-existing symptoms (numbness, pain or a burning feeling in the feet or hands) and/or signs of peripheral neuropathy may experience worsening peripheral neuropathy (including ≥ Grade 3) during treatment with bortezomib. Patients should be monitored for symptoms of neuropathy, such as a burning sensation, hyperesthesia, hypoesthesia, paresthesia, discomfort, neuropathic pain or weakness. In the Phase 3 relapsed multiple myeloma trial comparing bortezomib subcutaneous vs intravenous, the incidence of Grade ≥ 2 peripheral neuropathy was 24% for subcutaneous and 39% for intravenous. Grade ≥ 3 peripheral neuropathy occurred in 6% of patients in the subcutaneous treatment group, compared with 15% in the intravenous treatment group [see Adverse Reactions (6.1)]. Starting bortezomib subcutaneously may be considered for patients with pre-existing or at high risk of peripheral neuropathy.

Patients experiencing new or worsening peripheral neuropathy during bortezomib therapy may require a decrease in the dose and/or a less dose-intense schedule [see Dosage and Administration (2.7)]. In the bortezomib vs dexamethasone Phase 3 relapsed multiple myeloma study, improvement in or resolution of peripheral neuropathy was reported in 48% of patients with ≥ Grade 2 peripheral neuropathy following dose adjustment or interruption. Improvement in or resolution of peripheral neuropathy was reported in 73% of patients who discontinued due to Grade 2 neuropathy or who had ≥ Grade 3 peripheral neuropathy in the Phase 2 multiple myeloma studies. The long-term outcome of peripheral neuropathy has not been studied in mantle cell lymphoma.

5.2 Hypotension

The incidence of hypotension (postural, orthostatic, and hypotension NOS) was 8% [see Adverse Reactions (6.1)]. These events are observed throughout therapy. Patients with a history of syncope, patients receiving medications known to be associated with hypotension, and patients who are dehydrated may be at increased risk of hypotension. Management of orthostatic/postural hypotension may include adjustment of antihypertensive medications, hydration, and administration of mineralocorticoids and/or sympathomimetics.

5.3 Cardiac Toxicity

Acute development or exacerbation of congestive heart failure and new onset of decreased left ventricular ejection fraction have occurred during bortezomib therapy, including reports in patients with no risk factors for decreased left ventricular ejection fraction [see Adverse Reactions (6.1)]. Patients with risk factors for, or existing heart disease should be frequently monitored. In the relapsed multiple myeloma study of bortezomib vs dexamethasone, the incidence of any treatment-related cardiac disorder was 8% and 5% in the bortezomib and dexamethasone groups, respectively. The incidence of adverse reactions suggestive of heart failure (acute pulmonary edema, pulmonary edema, cardiac failure, congestive cardiac failure, cardiogenic shock) was ≤ 1% for each individual reaction in the bortezomib group. In the dexamethasone group the incidence was ≤ 1% for cardiac failure and congestive cardiac failure; there were no reported reactions of acute pulmonary edema, pulmonary edema, or cardiogenic shock. There have been isolated cases of QT-interval prolongation in clinical studies; causality has not been established.

5.4 Pulmonary Toxicity

Acute Respiratory Distress Syndrome (ARDS) and acute diffuse infiltrative pulmonary disease of unknown etiology such as pneumonitis, interstitial pneumonia, lung infiltration have occurred in patients receiving BORUZU. Some of these events have been fatal.

In a clinical trial, the first two patients given high-dose cytarabine (2 g/m^2 per day) by continuous infusion with daunorubicin and bortezomib for relapsed acute myelogenous leukemia died of ARDS early in the course of therapy.

There have been reports of pulmonary hypertension associated with bortezomib administration in the absence of left heart failure or significant pulmonary disease.

In the event of new or worsening cardiopulmonary symptoms, consider interrupting bortezomib until a prompt and comprehensive diagnostic evaluation is conducted.

5.5 Posterior Reversible Encephalopathy Syndrome (PRES)

Posterior Reversible Encephalopathy Syndrome (PRES; formerly termed Reversible Posterior Leukoencephalopathy Syndrome (RPLS)) has occurred in patients receiving BORUZU. PRES is a rare, reversible, neurological disorder which can present with seizure, hypertension, headache, lethargy, confusion, blindness, and other visual and neurological disturbances. Brain imaging, preferably MRI (Magnetic Resonance Imaging), is used to confirm the diagnosis. In patients developing PRES, discontinue BORUZU. The safety of reinitiating BORUZU therapy in patients previously experiencing PRES is not known.

5.6 Gastrointestinal Toxicity

BORUZU treatment can cause nausea, diarrhea, constipation, and vomiting [see Adverse Reactions (6.1)] sometimes requiring use of antiemetic and antidiarrheal medications. Ileus can occur. Fluid and electrolyte replacement should be administered to prevent dehydration. Interrupt BORUZU for severe symptoms.

5.7 Thrombocytopenia/Neutropenia

Bortezomib is associated with thrombocytopenia and neutropenia that follow a cyclical pattern with nadirs occurring following the last dose of each cycle and typically recovering prior to initiation of the subsequent cycle. The cyclical pattern of platelet and neutrophil decreases and recovery remain consistent in the studies of multiple myeloma and mantle cell lymphoma, with no evidence of cumulative thrombocytopenia or neutropenia in the treatment regimens studied.

Monitor complete blood counts (CBC) frequently during treatment with BORUZU. Measure platelet counts prior to each dose of BORUZU. Adjust dose/schedule for thrombocytopenia [see Dosage and Administration (2.6)]. Gastrointestinal and intracerebral hemorrhage has occurred during thrombocytopenia in association with BORUZU. Support with transfusions and supportive care, according to published guidelines.

In the single agent, relapsed multiple myeloma study of bortezomib vs dexamethasone, the mean platelet count nadir measured was approximately 40% of baseline. The severity of thrombocytopenia related to pretreatment platelet count is shown in Table 8. The incidence of bleeding (≥ Grade 3) was 2% on the bortezomib arm and was < 1% in the dexamethasone arm.

Table 8: Severity of Thrombocytopenia Related to Pretreatment Platelet Count in the Relapsed Multiple Myeloma Study of Bortezomib vs Dexamethasone

Pretreatment; Platelet Count* | Number of Patients (N=331)‡ | Number (%) of Patients with Platelet Count < 10,000/μL | Number (%) of Patients with Platelet Count; 10,000 to 25,000/μL
≥ 75,000/μL | 309 | 8 (3%) | 36 (12%)
≥ 50,000/μL to < 75,000/μL | 14 | 2 (14%) | 11 (79%)
≥ 10,000/μL to < 50,000/μL | 7 | 1 (14%) | 5 (71%)
* A baseline platelet count of 50,000/μL was required for study eligibility
‡ Data were missing at baseline for one patient

In the combination study of bortezomib with rituximab, cyclophosphamide, doxorubicin and prednisone (BR-CAP) in previously untreated mantle cell lymphoma patients, the incidence of thrombocytopenia (≥ Grade 4) was 32% vs 1% for the rituximab, cyclophosphamide, doxorubicin, vincristine, and prednisone (R-CHOP) arm as shown in Table 12. The incidence of bleeding events (≥ Grade 3) was 1.7% in the BR-CAP arm (four patients) and was 1.2% in the R-CHOP arm (three patients).

Platelet transfusions were given to 23% of the patients in the BR-CAP arm and 3% of the patients in the R-CHOP arm.

The incidence of neutropenia (≥ Grade 4) was 70% in the BR-CAP arm and was 52% in the R-CHOP arm. The incidence of febrile neutropenia (≥ Grade 4) was 5% in the BR-CAP arm and was 6% in the R-CHOP arm. Myeloid growth factor support was provided at a rate of 78% in the BR-CAP arm and 61% in the R-CHOP arm.

5.8 Tumor Lysis Syndrome

Tumor lysis syndrome has been reported with BORUZU therapy. Patients at risk of tumor lysis syndrome are those with high tumor burden prior to treatment. Monitor patients closely and take appropriate precautions.

5.9 Hepatic Toxicity

Cases of acute liver failure have been reported in patients receiving multiple concomitant medications and with serious underlying medical conditions. Other reported hepatic reactions include hepatitis, increases in liver enzymes, and hyperbilirubinemia. Interrupt BORUZU therapy to assess reversibility. There is limited rechallenge information in these patients.

5.10 Thrombotic Microangiopathy

Cases, sometimes fatal, of thrombotic microangiopathy, including thrombotic thrombocytopenic purpura/hemolytic uremic syndrome (TTP/HUS), have been reported in the postmarketing setting in patients who received bortezomib. Monitor for signs and symptoms of TTP/HUS. If the diagnosis is suspected, stop bortezomib and evaluate. If the diagnosis of TTP/HUS is excluded, consider restarting bortezomib. The safety of reinitiating bortezomib therapy in patients previously experiencing TTP/HUS is not known.

5.11 Embryo-Fetal Toxicity

Based on the mechanism of action and findings in animals, bortezomib can cause fetal harm when administered to a pregnant woman. Bortezomib administered to rabbits during organogenesis at a dose approximately 0.5 times the clinical dose of 1.3 mg/m^2 based on body surface area caused postimplantation loss and a decreased number of live fetuses [see Use in Specific Populations (8.1)].

Advise females of reproductive potential to use effective contraception during treatment with BORUZU and for seven months following treatment. Advise males with female partners of reproductive potential to use effective contraception during treatment with BORUZU and for four months following treatment. If BORUZU is used during pregnancy or if the patient becomes pregnant during BORUZU treatment, the patient should be apprised of the potential risk to the fetus [see Use in Specific Populations (8.1, 8.3), Nonclinical Toxicology (13.1)].

6 ADVERSE REACTIONS

The following clinically significant adverse reactions are also discussed in other sections of the labeling:

- Peripheral Neuropathy [see Warnings and Precautions (5.1)]
- Hypotension [see Warnings and Precautions (5.2)]
- Cardiac Toxicity [see Warnings and Precautions (5.3)]
- Pulmonary Toxicity [see Warnings and Precautions (5.4)]
- Posterior Reversible Encephalopathy Syndrome (PRES) [see Warnings and Precautions (5.5)]
- Gastrointestinal Toxicity [see Warnings and Precautions (5.6)]
- Thrombocytopenia/Neutropenia [see Warnings and Precautions (5.7)]
- Tumor Lysis Syndrome [see Warnings and Precautions (5.8)]
- Hepatic Toxicity [see Warnings and Precautions (5.9)]
- Thrombotic Microangiopathy [see Warnings and Precautions (5.10)]

6.1 Clinical Trials Experience

Because clinical trials are conducted under widely varying conditions, adverse reaction rates observed in the clinical trials of a drug cannot be directly compared to rates in the clinical trials of another drug and may not reflect the rates observed in clinical practice.

Summary of Clinical Trial in Patients with Previously Untreated Multiple Myeloma

Table 9 describes safety data from 340 patients with previously untreated multiple myeloma who received bortezomib (1.3 mg/m^2) administered intravenously in combination with melphalan (9 mg/m^2) and prednisone (60 mg/m^2) in a prospective randomized study.

The safety profile of bortezomib in combination with melphalan/prednisone is consistent with the known safety profiles of both bortezomib and melphalan/prednisone.

Table 9: Most Commonly Reported Adverse Reactions (≥ 10% in the Bortezomib, Melphalan and Prednisone Arm) with Grades 3 and ≥ 4 Intensity in the Previously Untreated Multiple Myeloma Study

 | Bortezomib, Melphalan and Prednisone; (n=340) |  |  | Melphalan and Prednisone; (n=337)
Body System | Total | Toxicity Grade,; n (%) |  | Total | Toxicity Grade,; n (%)
Adverse Reaction | n (%) | 3 | ≥ 4 | n (%) | 3 | ≥ 4
Blood and Lymphatic System Disorders
Thrombocytopenia | 164 (48) | 60 (18) | 57 (17) | 140 (42) | 48 (14) | 39 (12)
Neutropenia | 160 (47) | 101 (30) | 33 (10) | 143 (42) | 77 (23) | 42 (12)
Anemia | 109 (32) | 41 (12) | 4 (1) | 156 (46) | 61 (18) | 18 (5)
Leukopenia | 108 (32) | 64 (19) | 8 (2) | 93 (28) | 53 (16) | 11 (3)
Lymphopenia | 78 (23) | 46 (14) | 17 (5) | 51 (15) | 26 (8) | 7 (2)
Gastrointestinal Disorders
Nausea | 134 (39) | 10 (3) | 0 | 70 (21) | 1 (< 1) | 0
Diarrhea | 119 (35) | 19 (6) | 2 (1) | 20 (6) | 1 (< 1) | 0
Vomiting | 87 (26) | 13 (4) | 0 | 41 (12) | 2 (1) | 0
Constipation | 77 (23) | 2 (1) | 0 | 14 (4) | 0 | 0
Abdominal pain upper | 34 (10) | 1 (< 1) | 0 | 20 (6) | 0 | 0
Nervous System Disorders
Peripheral neuropathy* | 156 (46) | 42 (12) | 2 (1) | 4 (1) | 0 | 0
Neuralgia | 117 (34) | 27 (8) | 2 (1) | 1 (< 1) | 0 | 0
Paresthesia | 42 (12) | 6 (2) | 0 | 4 (1) | 0 | 0
General Disorders and Administration Site Conditions
Fatigue | 85 (25) | 19 (6) | 2 (1) | 48 (14) | 4 (1) | 0
Asthenia | 54 (16) | 18 (5) | 0 | 23 (7) | 3 (1) | 0
Pyrexia | 53 (16) | 4 (1) | 0 | 19 (6) | 1 (< 1) | 1 (< 1)
Infections and Infestations
Herpes Zoster | 39 (11) | 11 (3) | 0 | 9 (3) | 4 (1) | 0
Metabolism and Nutrition Disorders
Anorexia | 64 (19) | 6 (2) | 0 | 19 (6) | 0 | 0
Skin and Subcutaneous Tissue Disorders
Rash | 38 (11) | 2 (1) | 0 | 7 (2) | 0 | 0
Psychiatric Disorders
Insomnia | 35 (10) | 1 (< 1) | 0 | 21 (6) | 0 | 0
* Represents High Level Term Peripheral Neuropathies NEC

Relapsed Multiple Myeloma Randomized Study of Bortezomib vs Dexamethasone

The safety data described below and in Table 10 reflect exposure to either bortezomib (n=331) or dexamethasone (n=332) in a study of patients with relapsed multiple myeloma. Bortezomib was administered intravenously at doses of 1.3 mg/m^2 twice weekly for two out of three weeks (21 day cycle). After eight, 21 day cycles patients continued therapy for three, 35 day cycles on a weekly schedule. Duration of treatment was up to 11 cycles (nine months) with a median duration of six cycles (4.1 months). For inclusion in the trial, patients must have had measurable disease and one to three prior therapies. There was no upper age limit for entry. Creatinine clearance could be as low as 20 mL/min and bilirubin levels as high as 1.5 times the upper limit of normal. The overall frequency of adverse reactions was similar in men and women, and in patients < 65 and ≥ 65 years of age. Most patients were Caucasian [see Clinical Studies (14.1)].

Among the 331 bortezomib-treated patients, the most commonly reported (> 20%) adverse reactions overall were nausea (52%), diarrhea (52%), fatigue (39%), peripheral neuropathies (35%), thrombocytopenia (33%), constipation (30%), vomiting (29%), and anorexia (21%). The most commonly reported (> 20%) adverse reaction reported among the 332 patients in the dexamethasone group was fatigue (25%). Eight percent (8%) of patients in the bortezomib-treated arm experienced a Grade 4 adverse reaction; the most common reactions were thrombocytopenia (4%) and neutropenia (2%). Nine percent (9%) of dexamethasone-treated patients experienced a Grade 4 adverse reaction. All individual dexamethasone-related Grade 4 adverse reactions were less than 1%.

Serious Adverse Reactions and Adverse Reactions Leading to Treatment Discontinuation in the Relapsed Multiple Myeloma Study of Bortezomib vs Dexamethasone

Serious adverse reactions are defined as any reaction that results in death, is life-threatening, requires hospitalization or prolongs a current hospitalization, results in a significant disability, or is deemed to be an important medical event. A total of 80 (24%) patients from the bortezomib treatment arm experienced a serious adverse reaction during the study, as did 83 (25%) dexamethasone-treated patients. The most commonly reported serious adverse reactions in the bortezomib treatment arm were diarrhea (3%), dehydration, herpes zoster, pyrexia, nausea, vomiting, dyspnea, and thrombocytopenia (2% each). In the dexamethasone treatment group, the most commonly reported serious adverse reactions were pneumonia (4%), hyperglycemia (3%), pyrexia, and psychotic disorder (2% each).

A total of 145 patients, including 84 (25%) of 331 patients in the bortezomib treatment group and 61 (18%) of 332 patients in the dexamethasone treatment group were discontinued from treatment due to adverse reactions. Among the 331 bortezomib-treated patients, the most commonly reported adverse reaction leading to discontinuation was peripheral neuropathy (8%). Among the 332 patients in the dexamethasone group, the most commonly reported adverse reactions leading to treatment discontinuation were psychotic disorder and hyperglycemia (2% each).

Four deaths were considered to be bortezomib-related in this relapsed multiple myeloma study: one case each of cardiogenic shock, respiratory insufficiency, congestive heart failure and cardiac arrest. Four deaths were considered dexamethasone-related: two cases of sepsis, one case of bacterial meningitis, and one case of sudden death at home.

Most Commonly Reported Adverse Reactions in the Relapsed Multiple Myeloma Study of Bortezomib vs Dexamethasone

The most common adverse reactions from the relapsed multiple myeloma study are shown in Table 10. All adverse reactions with incidence ≥ 10% in the bortezomib arm are included.

Table 10: Most Commonly Reported Adverse Reactions (≥ 10% in Bortezomib Arm), with Grades 3 and 4 Intensity in the Relapsed Multiple Myeloma Study of Bortezomib vs Dexamethasone (N=663)

Adverse Reactions | Bortezomib; (N=331) |  |  | Dexamethasone; (N=332)
Adverse Reactions | All | Grade 3 | Grade 4 | All | Grade 3 | Grade 4
Any Adverse Reactions | 324 (98) | 193 (58) | 28 (8) | 297 (89) | 110 (33) | 29 (9)
Nausea | 172 (52) | 8 (2) | 0 | 31 (9) | 0 | 0
Diarrhea NOS | 171 (52) | 22 (7) | 0 | 36 (11) | 2 (< 1) | 0
Fatigue | 130 (39) | 15 (5) | 0 | 82 (25) | 8 (2) | 0
Peripheral neuropathies* | 115 (35) | 23 (7) | 2 (< 1) | 14 (4) | 0 | 1 (< 1)
Thrombocytopenia | 109 (33) | 80 (24) | 12 (4) | 11 (3) | 5 (2) | 1 (< 1)
Constipation | 99 (30) | 6 (2) | 0 | 27 (8) | 1 (< 1) | 0
Vomiting NOS | 96 (29) | 8 (2) | 0 | 10 (3) | 1 (< 1) | 0
Anorexia | 68 (21) | 8 (2) | 0 | 8 (2) | 1 (< 1) | 0
Pyrexia | 66 (20) | 2 (< 1) | 0 | 21 (6) | 3 (< 1) | 1 (< 1)
Paresthesia | 64 (19) | 5 (2) | 0 | 24 (7) | 0 | 0
Anemia NOS | 63 (19) | 20 (6) | 1 (< 1) | 21 (6) | 8 (2) | 0
Headache NOS | 62 (19) | 3 (< 1) | 0 | 23 (7) | 1 (< 1) | 0
Neutropenia | 58 (18) | 37 (11) | 8 (2) | 1 (< 1) | 1 (< 1) | 0
Rash NOS | 43 (13) | 3 (< 1) | 0 | 7 (2) | 0 | 0
Appetite decreased NOS | 36 (11) | 0 | 0 | 12 (4) | 0 | 0
Dyspnea NOS | 35 (11) | 11 (3) | 1 (< 1) | 37 (11) | 7 (2) | 1 (< 1)
Abdominal pain NOS | 35 (11) | 5 (2) | 0 | 7 (2) | 0 | 0
Weakness | 34 (10) | 10 (3) | 0 | 28 (8) | 8 (2) | 0
*Represents High Level Term Peripheral Neuropathies NEC

Safety Experience from the Phase 2 Open-Label Extension Study in Relapsed Multiple Myeloma

In the Phase 2 extension study of 63 patients, no new cumulative or new long-term toxicities were observed with prolonged bortezomib treatment. These patients were treated for a total of 5.3 to 23 months, including time on bortezomib in the prior bortezomib study [see Clinical Studies (14.1)].

Safety Experience from the Phase 3 Open-Label Study of Bortezomib Subcutaneous vs Intravenous in Relapsed Multiple Myeloma

The safety and efficacy of bortezomib administered subcutaneously were evaluated in one Phase 3 study at the recommended dose of 1.3 mg/m^2. This was a randomized, comparative study of bortezomib subcutaneous vs intravenous in 222 patients with relapsed multiple myeloma. The safety data described below and in Table 11 reflect exposure to either bortezomib subcutaneous (N=147) or bortezomib intravenous (N=74) [see Clinical Studies (14.1)].

Table 11: Most Commonly Reported Adverse Reactions (≥ 10%), with Grade 3 and ≥ 4 Intensity in the Relapsed Multiple Myeloma Study (N=221) of Bortezomib Subcutaneous vs Intravenous

 | Subcutaneous |  |  | Intravenous
 | (N=147) |  |  | (N=74)
Body System | Total | Toxicity Grade,; n (%) |  | Total | Toxicity Grade,; n (%)
Adverse Reaction | n (%) | 3 | ≥ 4 | n (%) | 3 | ≥ 4
Blood and Lymphatic System Disorders
Anemia | 28 (19) | 8 (5) | 0 | 17 (23) | 3 (4) | 0
Leukopenia | 26 (18) | 8 (5) | 0 | 15 (20) | 4 (5) | 1 (1)
Neutropenia | 34 (23) | 15 (10) | 4 (3) | 20 (27) | 10 (14) | 3 (4)
Thrombocytopenia | 44 (30) | 7 (5) | 5 (3) | 25 (34) | 7 (9) | 5 (7)
Gastrointestinal Disorders
Diarrhea | 28 (19) | 1 (1) | 0 | 21 (28) | 3 (4) | 0
Nausea | 24 (16) | 0 | 0 | 10 (14) | 0 | 0
Vomiting | 13 (9) | 3 (2) | 0 | 8 (11) | 0 | 0
General Disorders and Administration Site Conditions
Asthenia | 10 (7) | 1 (1) | 0 | 12 (16) | 4 (5) | 0
Fatigue | 11 (7) | 3 (2) | 0 | 11 (15) | 3 (4) | 0
Pyrexia | 18 (12) | 0 | 0 | 6 (8) | 0 | 0
Nervous System Disorders
Neuralgia | 34 (23) | 5 (3) | 0 | 17 (23) | 7 (9) | 0
Peripheral neuropathies* | 55 (37) | 8 (5) | 1 (1) | 37 (50) | 10 (14) | 1 (1)
Note: Safety population: 147 patients in the subcutaneous treatment group and 74 patients in the intravenous treatment group who received at least one dose of study medication
* Represents High Level Term Peripheral Neuropathies NEC

In general, safety data were similar for the subcutaneous and intravenous treatment groups. Differences were observed in the rates of some Grade ≥ 3 adverse reactions. Differences of ≥ 5% were reported in neuralgia (3% subcutaneous vs 9% intravenous), peripheral neuropathies (6% subcutaneous vs 15% intravenous), neutropenia (13% subcutaneous vs 18% intravenous), and thrombocytopenia (8% subcutaneous vs 16% intravenous).

A local reaction was reported in 6% of patients in the subcutaneous group, mostly redness. Only two (1%) patients were reported as having severe reactions, one case of pruritus and one case of redness. Local reactions led to reduction in injection concentration in one patient and drug discontinuation in one patient. Local reactions resolved in a median of six days.

Dose reductions occurred due to adverse reactions in 31% of patients in the subcutaneous treatment group compared with 43% of the intravenously-treated patients. The most common adverse reactions leading to a dose reduction included peripheral sensory neuropathy (17% in the subcutaneous treatment group compared with 31% in the intravenous treatment group); and neuralgia (11% in the subcutaneous treatment group compared with 19% in the intravenous treatment group).

Serious Adverse Reactions and Adverse Reactions Leading to Treatment Discontinuation in the Relapsed Multiple Myeloma Study of Bortezomib Subcutaneous vs Intravenous

The incidence of serious adverse reactions was similar for the subcutaneous treatment group (20%) and the intravenous treatment group (19%). The most commonly reported serious adverse reactions in the subcutaneous treatment arm were pneumonia and pyrexia (2% each). In the intravenous treatment group, the most commonly reported serious adverse reactions were pneumonia, diarrhea, and peripheral sensory neuropathy (3% each).

In the subcutaneous treatment group, 27 patients (18%) discontinued study treatment due to an adverse reaction compared with 17 patients (23%) in the intravenous treatment group. Among the 147 subcutaneously-treated patients, the most commonly reported adverse reactions leading to discontinuation were peripheral sensory neuropathy (5%) and neuralgia (5%). Among the 74 patients in the intravenous treatment group, the most commonly reported adverse reactions leading to treatment discontinuation were peripheral sensory neuropathy (9%) and neuralgia (9%).

Two patients (1%) in the subcutaneous treatment group and one (1%) patient in the intravenous treatment group died due to an adverse reaction during treatment. In the subcutaneous group the causes of death were one case of pneumonia and one case of sudden death. In the intravenous group the cause of death was coronary artery insufficiency.

Safety Experience from the Clinical Trial in Patients with Previously Untreated Mantle Cell Lymphoma

Table 12 describes safety data from 240 patients with previously untreated mantle cell lymphoma who received bortezomib (1.3 mg/m^2) administered intravenously in combination with rituximab (375 mg/m^2), cyclophosphamide (750 mg/m^2), doxorubicin (50 mg/m^2), and prednisone (100 mg/m^2) (BR-CAP) in a prospective randomized study.

Infections were reported for 31% of patients in the BR-CAP arm and 23% of the patients in the comparator (rituximab, cyclophosphamide, doxorubicin, vincristine, and prednisone [R-CHOP]) arm, including the predominant preferred term of pneumonia (BR-CAP 8% vs R-CHOP 5%).

Table 12: Most Commonly Reported Adverse Reactions (≥ 5%) with Grades 3 and ≥ 4 Intensity in the Previously Untreated Mantle Cell Lymphoma Study

 | BR-CAP (n=240) |  |  | R-CHOP (n=242)
Body System Adverse Reactions | All n (%) | Toxicity Grade 3 n (%) | Toxicity Grade ≥ 4n (%) | All n (%) | Toxicity Grade 3n (%) | Toxicity Grade ≥ 4n (%)
Blood and Lymphatic System Disorders
Neutropenia | 209 (87) | 32 (13) | 168 (70) | 172 (71) | 31 (13) | 125 (52)
Leukopenia | 116 (48) | 34 (14) | 69 (29) | 87 (36) | 39 (16) | 27 (11)
Anemia | 106 (44) | 27 (11) | 4 (2) | 71 (29) | 23 (10) | 4 (2)
Thrombocytopenia | 172 (72) | 59 (25) | 76 (32) | 42 (17) | 9 (4) | 3 (1)
Febrile neutropenia | 41 (17) | 24 (10) | 12 (5) | 33 (14) | 17 (7) | 15 (6)
Lymphopenia | 68 (28) | 25 (10) | 36 (15) | 28 (12) | 15 (6) | 2 (1)
Nervous System Disorders
Peripheral neuropathy* | 71 (30) | 17 (7) | 1 (< 1) | 65 (27) | 10 (4) | 0
Hypoesthesia | 14 (6) | 3 (1) | 0 | 13 (5) | 0 | 0
Paresthesia | 14 (6) | 2 (1) | 0 | 11 (5) | 0 | 0
Neuralgia | 25 (10) | 9 (4) | 0 | 1 (< 1) | 0 | 0
General Disorders and Administration Site Conditions
Fatigue | 43 (18) | 11 (5) | 1 (< 1) | 38 (16) | 5 (2) | 0
Pyrexia | 48 (20) | 7 (3) | 0 | 23 (10) | 5 (2) | 0
Asthenia | 29 (12) | 4 (2) | 1 (< 1) | 18 (7) | 1 (< 1) | 0
Edema peripheral | 16 (7) | 1 (< 1) | 0 | 13 (5) | 0 | 0
Gastrointestinal Disorders
Nausea | 54 (23) | 1 (< 1) | 0 | 28 (12) | 0 | 0
Constipation | 42 (18) | 1 (< 1) | 0 | 22 (9) | 2 (1) | 0
Stomatitis | 20 (8) | 2 (1) | 0 | 19 (8) | 0 | 1 (< 1)
Diarrhea | 59 (25) | 11 (5) | 0 | 11 (5) | 3 (1) | 1 (< 1)
Vomiting | 24 (10) | 1 (< 1) | 0 | 8 (3) | 0 | 0
Abdominal distension | 13 (5) | 0 | 0 | 4 (2) | 0 | 0
Infections and Infestations
Pneumonia | 20 (8) | 8 (3) | 5 (2) | 11 (5) | 5 (2) | 3 (1)
Skin and Subcutaneous Tissue Disorders
Alopecia | 31 (13) | 1 (< 1) | 1 (< 1) | 33 (14) | 4 (2) | 0
Metabolism and Nutrition Disorders
Hyperglycemia | 10 (4) | 1 (< 1) | 0 | 17 (7) | 10 (4) | 0
Decreased appetite | 36 (15) | 2 (1) | 0 | 15 (6) | 1 (< 1) | 0
Vascular Disorders
Hypertension | 15 (6) | 1 (< 1) | 0 | 3 (1) | 0 | 0
Psychiatric Disorders
Insomnia | 16 (7) | 1 (< 1) | 0 | 8 (3) | 0 | 0
Key: R-CHOP = rituximab, cyclophosphamide, doxorubicin, vincristine, and prednisone; BR-CAP = bortezomib, rituximab, cyclophosphamide, doxorubicin, and prednisone.
* Represents High Level Term Peripheral Neuropathies NEC

The incidence of herpes zoster reactivation was 4.6% in the BR-CAP arm and 0.8% in the R-CHOP arm. Antiviral prophylaxis was mandated by protocol amendment.

The incidences of Grade ≥ 3 bleeding events were similar between the two arms (four patients in the BR-CAP arm and three patients in the R-CHOP arm). All of the Grade ≥ 3 bleeding events resolved without sequelae in the BR-CAP arm.

Adverse reactions leading to discontinuation occurred in 8% of patients in BR-CAP group and 6% of patients in R-CHOP group. In the BR-CAP group, the most commonly reported adverse reaction leading to discontinuation was peripheral sensory neuropathy (1%; three patients). The most commonly reported adverse reaction leading to discontinuation in the R-CHOP group was febrile neutropenia (< 1%; two patients).

Integrated Summary of Safety (Relapsed Multiple Myeloma and Relapsed Mantle Cell Lymphoma)

Safety data from Phase 2 and 3 studies of single agent bortezomib 1.3 mg/m^2/dose twice weekly for two weeks followed by a ten day rest period in 1163 patients with previously-treated multiple myeloma (N=1008) and previously-treated mantle cell lymphoma (N=155) were integrated and tabulated. This analysis does not include data from the Phase 3 open-label study of bortezomib subcutaneous vs intravenous in relapsed multiple myeloma. In the integrated studies, the safety profile of bortezomib was similar in patients with multiple myeloma and mantle cell lymphoma.

In the integrated analysis, the most commonly reported (> 20%) adverse reactions were nausea (49%), diarrhea (46%), asthenic conditions including fatigue (41%) and weakness (11%), peripheral neuropathies (38%), thrombocytopenia (32%), vomiting (28%), constipation (25%), and pyrexia (21%). Eleven percent (11%) of patients experienced at least one episode of ≥ Grade 4 toxicity, most commonly thrombocytopenia (4%) and neutropenia (2%).

In the Phase 2 relapsed multiple myeloma clinical trials of bortezomib administered intravenously, local skin irritation was reported in 5% of patients, but extravasation of bortezomib was not associated with tissue damage.

Serious Adverse Reactions and Adverse Reactions Leading to Treatment Discontinuation in the Integrated Summary of Safety

A total of 26% of patients experienced a serious adverse reaction during the studies. The most commonly reported serious adverse reactions included diarrhea, vomiting and pyrexia (3% each), nausea, dehydration, and thrombocytopenia (2% each) and pneumonia, dyspnea, peripheral neuropathies, and herpes zoster (1% each).

Adverse reactions leading to discontinuation occurred in 22% of patients. The reasons for discontinuation included peripheral neuropathy (8%), and fatigue, thrombocytopenia, and diarrhea (2% each).

In total, 2% of the patients died and the cause of death was considered by the investigator to be possibly related to study drug: including reports of cardiac arrest, congestive heart failure, respiratory failure, renal failure, pneumonia and sepsis.

Most Commonly Reported Adverse Reactions in the Integrated Summary of Safety

The most common adverse reactions are shown in Table 13. All adverse reactions occurring at ≥ 10% are included. In the absence of a randomized comparator arm, it is often not possible to distinguish between adverse events that are drug-caused and those that reflect the patient’s underlying disease. Please see the discussion of specific adverse reactions that follows.

Table 13: Most Commonly Reported (≥ 10% Overall) Adverse Reactions in Integrated Analyses of Relapsed Multiple Myeloma and Relapsed Mantle Cell Lymphoma Studies Using the 1.3 mg/m^2 Dose (N=1163)

 | All Patients (N=1163) |  | Multiple Myeloma (N=1008) |  | Mantle Cell Lymphoma (N=155)
Adverse Reactions | All | ≥ Grade 3 | All | ≥ Grade 3 | All | ≥ Grade 3
Nausea | 567 (49) | 36 (3) | 511 (51) | 32 (3) | 56 (36) | 4 (3)
Diarrhea NOS | 530 (46) | 83 (7) | 470 (47) | 72 (7) | 60 (39) | 11 (7)
Fatigue | 477 (41) | 86 (7) | 396 (39) | 71 (7) | 81 (52) | 15 (10)
Peripheral neuropathies* | 443 (38) | 129 (11) | 359 (36) | 110 (11) | 84 (54) | 19 (12)
Thrombocytopenia | 369 (32) | 295 (25) | 344 (34) | 283 (28) | 25 (16) | 12 (8)
Vomiting NOS | 321 (28) | 44 (4) | 286 (28) | 40 (4) | 35 (23) | 4 (3)
Constipation | 296 (25) | 17 (1) | 244 (24) | 14 (1) | 52 (34) | 3 (2)
Pyrexia | 249 (21) | 16 (1) | 233 (23) | 15 (1) | 16 (10) | 1 (< 1)
Anorexia | 227 (20) | 19 (2) | 205 (20) | 16 (2) | 22 (14) | 3 (2)
Anemia NOS | 209 (18) | 65 (6) | 190 (19) | 63 (6) | 19 (12) | 2 (1)
Headache NOS | 175 (15) | 8 (< 1) | 160 (16) | 8 (< 1) | 15 (10) | 0
Neutropenia | 172 (15) | 121 (10) | 164 (16) | 117 (12) | 8 (5) | 4 (3)
Rash NOS | 156 (13) | 8 (< 1) | 120 (12) | 4 (< 1) | 36 (23) | 4 (3)
Paresthesia | 147 (13) | 9 (< 1) | 136 (13) | 8 (< 1) | 11 (7) | 1 (< 1)
Dizziness (excl vertigo) | 129 (11) | 13 (1) | 101 (10) | 9 (< 1) | 28 (18) | 4 (3)
Weakness | 124 (11) | 31 (3) | 106 (11) | 28 (3) | 18 (12) | 3 (2)
* Represents High Level Term Peripheral Neuropathies NEC

Description of Selected Adverse Reactions from the Integrated Phase 2 and 3 Relapsed Multiple Myeloma and Phase 2 Relapsed Mantle Cell Lymphoma Studies

Gastrointestinal Toxicity

A total of 75% of patients experienced at least one gastrointestinal disorder. The most common gastrointestinal disorders included nausea, diarrhea, constipation, vomiting, and appetite decreased. Other gastrointestinal disorders included dyspepsia and dysgeusia. Grade 3 adverse reactions occurred in 14% of patients; ≥ Grade 4 adverse reactions were ≤ 1%. Gastrointestinal adverse reactions were considered serious in 7% of patients. Four percent (4%) of patients discontinued due to a gastrointestinal adverse reaction. Nausea was reported more often in patients with multiple myeloma (51%) compared to patients with mantle cell lymphoma (36%).

Thrombocytopenia

Across the studies, bortezomib-associated thrombocytopenia was characterized by a decrease in platelet count during the dosing period (Days 1 to 11) and a return toward baseline during the ten day rest period during each treatment cycle. Overall, thrombocytopenia was reported in 32% of patients. Thrombocytopenia was Grade 3 in 22%, ≥ Grade 4 in 4%, and serious in 2% of patients, and the reaction resulted in bortezomib discontinuation in 2% of patients [see Warnings and Precautions (5.7)]. Thrombocytopenia was reported more often in patients with multiple myeloma (34%) compared to patients with mantle cell lymphoma (16%). The incidence of ≥ Grade 3 thrombocytopenia also was higher in patients with multiple myeloma (28%) compared to patients with mantle cell lymphoma (8%).

Peripheral Neuropathy

Overall, peripheral neuropathies occurred in 38% of patients. Peripheral neuropathy was Grade 3 for 11% of patients and ≥ Grade 4 for < 1% of patients. Eight percent (8%) of patients discontinued bortezomib due to peripheral neuropathy. The incidence of peripheral neuropathy was higher among patients with mantle cell lymphoma (54%) compared to patients with multiple myeloma (36%).

In the bortezomib vs dexamethasone Phase 3 relapsed multiple myeloma study, among the 62 bortezomib-treated patients who experienced ≥ Grade 2 peripheral neuropathy and had dose adjustments, 48% had improved or resolved with a median of 3.8 months from first onset.

In the Phase 2 relapsed multiple myeloma studies, among the 30 patients who experienced Grade 2 peripheral neuropathy resulting in discontinuation or who experienced ≥ Grade 3 peripheral neuropathy, 73% reported improvement or resolution with a median time of 47 days to improvement of one grade or more from the last dose of bortezomib.

Hypotension

The incidence of hypotension (postural, orthostatic and hypotension NOS) was 8% in patients treated with bortezomib. Hypotension was Grade 1 or 2 in the majority of patients and Grade 3 in 2% and ≥ Grade 4 in < 1%. Two percent (2%) of patients had hypotension reported as a serious adverse reaction, and 1% discontinued due to hypotension. The incidence of hypotension was similar in patients with multiple myeloma (8%) and those with mantle cell lymphoma (9%). In addition, < 1% of patients experienced hypotension associated with a syncopal reaction.

Neutropenia

Neutrophil counts decreased during the bortezomib dosing period (Days 1 to 11) and returned toward baseline during the ten day rest period during each treatment cycle. Overall, neutropenia occurred in 15% of patients and was Grade 3 in 8% of patients and ≥ Grade 4 in 2%. Neutropenia was reported as a serious adverse reaction in < 1% of patients and < 1% of patients discontinued due to neutropenia. The incidence of neutropenia was higher in patients with multiple myeloma (16%) compared to patients with mantle cell lymphoma (5%). The incidence of ≥ Grade 3 neutropenia also was higher in patients with multiple myeloma (12%) compared to patients with mantle cell lymphoma (3%).

Asthenic Conditions (Fatigue, Malaise, Weakness, Asthenia)

Asthenic conditions were reported in 54% of patients. Fatigue was reported as Grade 3 in 7% and ≥ Grade 4 in < 1% of patients. Asthenia was reported as Grade 3 in 2% and ≥ Grade 4 in < 1% of patients. Two percent (2%) of patients discontinued treatment due to fatigue and < 1% due to weakness and asthenia. Asthenic conditions were reported in 53% of patients with multiple myeloma and 59% of patients with mantle cell lymphoma.

Pyrexia

Pyrexia (> 38○C) was reported as an adverse reaction for 21% of patients. The reaction was Grade 3 in 1% and ≥ Grade 4 in < 1%. Pyrexia was reported as a serious adverse reaction in 3% of patients and led to bortezomib discontinuation in < 1% of patients. The incidence of pyrexia was higher among patients with multiple myeloma (23%) compared to patients with mantle cell lymphoma (10%). The incidence of ≥ Grade 3 pyrexia was 1% in patients with multiple myeloma and < 1% in patients with mantle cell lymphoma.

Herpes Virus Infection

Consider using antiviral prophylaxis in subjects being treated with bortezomib. In the randomized studies in previously untreated and relapsed multiple myeloma, herpes zoster reactivation was more common in subjects treated with bortezomib (ranging between 6 to 11%) than in the control groups (3 to 4%). Herpes simplex was seen in 1 to 3% in subjects treated with bortezomib and 1 to 3% in the control groups. In the previously untreated multiple myeloma study, herpes zoster virus reactivation in the bortezomib, melphalan and prednisone arm was less common in subjects receiving prophylactic antiviral therapy (3%) than in subjects who did not receive prophylactic antiviral therapy (17%).

Retreatment in Relapsed Multiple Myeloma

A single-arm trial was conducted in 130 patients with relapsed multiple myeloma to determine the efficacy and safety of retreatment with intravenous bortezomib. The safety profile of patients in this trial is consistent with the known safety profile of bortezomib-treated patients with relapsed multiple myeloma as demonstrated in Tables 10, 11, and 13; no cumulative toxicities were observed upon retreatment. The most common adverse drug reaction was thrombocytopenia which occurred in 52% of the patients. The incidence of ≥ Grade 3 thrombocytopenia was 24%. Peripheral neuropathy occurred in 28% of patients, with the incidence of ≥ Grade 3 peripheral neuropathy reported at 6%. The incidence of serious adverse reactions was 12.3%. The most commonly reported serious adverse reactions were thrombocytopenia (3.8%), diarrhea (2.3%), and herpes zoster and pneumonia (1.5% each).

Adverse reactions leading to discontinuation occurred in 13% of patients. The reasons for discontinuation included peripheral neuropathy (5%) and diarrhea (3%).

Two deaths considered to be bortezomib-related occurred within 30 days of the last bortezomib dose; one in a patient with cerebrovascular accident and one in a patient with sepsis.

Additional Adverse Reactions from Clinical Studies

The following clinically important serious adverse reactions that are not described above have been reported in clinical trials in patients treated with bortezomib administered as monotherapy or in combination with other chemotherapeutics. These studies were conducted in patients with hematological malignancies and in solid tumors.

Blood and Lymphatic System Disorders: Anemia, disseminated intravascular coagulation, febrile neutropenia, lymphopenia, leukopenia

Cardiac Disorders: Angina pectoris, atrial fibrillation aggravated, atrial flutter, bradycardia, sinus arrest, cardiac amyloidosis, complete atrioventricular block, myocardial ischemia, myocardial infarction, pericarditis, pericardial effusion, Torsades de pointes, ventricular tachycardia

Ear and Labyrinth Disorders: Hearing impaired, vertigo

Eye Disorders: Diplopia and blurred vision, conjunctival infection, irritation

Gastrointestinal Disorders: Abdominal pain, ascites, dysphagia, fecal impaction, gastroenteritis, gastritis hemorrhagic, hematemesis, hemorrhagic duodenitis, ileus paralytic, large intestinal obstruction, paralytic intestinal obstruction, peritonitis, small intestinal obstruction, large intestinal perforation, stomatitis, melena, pancreatitis acute, oral mucosal petechiae, gastroesophageal reflux

General Disorders and Administration Site Conditions: Chills, edema, edema peripheral, injection site erythema, neuralgia, injection site pain, irritation, malaise, phlebitis

Hepatobiliary Disorders: Cholestasis, hepatic hemorrhage, hyperbilirubinemia, portal vein thrombosis, hepatitis, liver failure

Immune System Disorders: Anaphylactic reaction, drug hypersensitivity, immune complex mediated hypersensitivity, angioedema, laryngeal edema

Infections and Infestations: Aspergillosis, bacteremia, bronchitis, urinary tract infection, herpes viral infection, listeriosis, nasopharyngitis, pneumonia, respiratory tract infection, septic shock, toxoplasmosis, oral candidiasis, sinusitis, catheter-related infection

Injury, Poisoning and Procedural Complications: Catheter-related complication, skeletal fracture, subdural hematoma

Investigations: Weight decreased

Metabolism and Nutrition Disorders: Dehydration, hypocalcemia, hyperuricemia, hypokalemia, hyperkalemia, hyponatremia, hypernatremia

Musculoskeletal and Connective Tissue Disorders: Arthralgia, back pain, bone pain, myalgia, pain in extremity

Nervous System Disorders: Ataxia, coma, dizziness, dysarthria, dysesthesia, dysautonomia, encephalopathy, cranial palsy, grand mal convulsion, headache, hemorrhagic stroke, motor dysfunction, neuralgia, spinal cord compression, paralysis, postherpetic neuralgia, transient ischemic attack

Psychiatric Disorders: Agitation, anxiety, confusion, insomnia, mental status change, psychotic disorder, suicidal ideation

Renal and Urinary Disorders: Calculus renal, bilateral hydronephrosis, bladder spasm, hematuria, hemorrhagic cystitis, urinary incontinence, urinary retention, renal failure (acute and chronic), glomerular nephritis proliferative

Respiratory, Thoracic and Mediastinal Disorders: Acute respiratory distress syndrome, aspiration pneumonia, atelectasis, chronic obstructive airways disease exacerbated, cough, dysphagia, dyspnea, dyspnea exertional, epistaxis, hemoptysis, hypoxia, lung infiltration, pleural effusion, pneumonitis, respiratory distress, pulmonary hypertension

Skin and Subcutaneous Tissue Disorders: Urticaria, face edema, rash (which may be pruritic), leukocytoclastic vasculitis, pruritus

Vascular Disorders: Cerebrovascular accident, cerebral hemorrhage, deep venous thrombosis, hypertension, peripheral embolism, pulmonary embolism, pulmonary hypertension

6.2 Postmarketing Experience

The following adverse reactions have been identified from the worldwide postmarketing experience with bortezomib. Because these reactions are reported voluntarily from a population of uncertain size, it is not always possible to reliably estimate their frequency or establish a causal relationship to drug exposure:

Cardiac Disorders: Cardiac tamponade

Ear and Labyrinth Disorders: Deafness bilateral

Eye Disorders: Optic neuropathy, blindness, chalazion/blepharitis

Gastrointestinal Disorders: Ischemic colitis

Infections and Infestations: Progressive multifocal leukoencephalopathy (PML), ophthalmic herpes, herpes meningoencephalitis

Nervous System Disorders: Posterior reversible encephalopathy syndrome (PRES, formerly RPLS), Guillain-Barre syndrome, demyelinating polyneuropathy

Respiratory, Thoracic and Mediastinal Disorders: Acute diffuse infiltrative pulmonary disease

Skin and Subcutaneous Tissue Disorders: Stevens-Johnson syndrome/toxic epidermal necrolysis (SJS/TEN), acute febrile neutrophilic dermatosis (Sweet’s syndrome)

7 DRUG INTERACTIONS

7.1 Effects of Other Drugs on BORUZU

Strong CYP3A4 Inducers

Coadministration with a strong CYP3A4 inducer decreases the exposure of bortezomib [see Clinical Pharmacology (12.3)] which may decrease bortezomib efficacy. Avoid coadministration with strong CYP3A4 inducers.

Strong CYP3A4 Inhibitors

Coadministration with a strong CYP3A4 inhibitor increases the exposure of bortezomib [see Clinical Pharmacology (12.3)] which may increase the risk of bortezomib toxicities. Monitor patients for signs of bortezomib toxicity and consider a bortezomib dose reduction if bortezomib must be given in combination with strong CYP3A4 inhibitors.

7.2 Drugs Without Clinically Significant Interactions with Bortezomib

No clinically significant drug interactions have been observed when bortezomib was coadministered with dexamethasone, omeprazole, or melphalan in combination with prednisone [see Clinical Pharmacology (12.3)].

8 USE IN SPECIFIC POPULATIONS

8.1 Pregnancy

Risk Summary

Based on its mechanism of action [see Clinical Pharmacology (12.1)] and findings in animals, bortezomib can cause fetal harm when administered to a pregnant woman. There are no studies with the use of bortezomib in pregnant women to inform drug-associated risks. Bortezomib caused embryo-fetal lethality in rabbits at doses lower than the clinical dose (see Data). Advise pregnant women of the potential risk to the fetus.

Adverse outcomes in pregnancy occur regardless of the health of the mother or the use of medications. The estimated background risk of major birth defects and miscarriage for the indicated population is unknown. In the U.S. general population, the estimated background risk of major birth defects and miscarriage in clinically recognized pregnancies is 2 to 4% and 15 to 20%, respectively.

Data

Animal Data

Bortezomib was not teratogenic in nonclinical developmental toxicity studies in rats and rabbits at the highest dose tested (0.075 mg/kg; 0.5 mg/m^2 in the rat and 0.05 mg/kg; 0.6 mg/m^2 in the rabbit) when administered during organogenesis. These dosages are approximately 0.5 times the clinical dose of 1.3 mg/m^2 based on body surface area.

Bortezomib caused embryo-fetal lethality in rabbits at doses lower than the clinical dose (approximately 0.5 times the clinical dose of 1.3 mg/m^2 based on body surface area). Pregnant rabbits given bortezomib during organogenesis at a dose of 0.05 mg/kg (0.6 mg/m^2) experienced significant postimplantation loss and decreased number of live fetuses. Live fetuses from these litters also showed significant decreases in fetal weight.

8.2 Lactation

Risk Summary

There are no data on the presence of bortezomib or its metabolites in human milk, the effects of the drug on the breastfed child, or the effects of the drug on milk production. Because many drugs are excreted in human milk and because the potential for serious adverse reactions in a breastfed child from bortezomib is unknown, advise nursing women not to breastfeed during treatment with bortezomib and for two months after treatment.

8.3 Females and Males of Reproductive Potential

Based on its mechanism of action and findings in animals, bortezomib can cause fetal harm when administered to a pregnant woman [see Use in Specific Populations (8.1)].

Pregnancy Testing

Conduct pregnancy testing in females of reproductive potential prior to initiating bortezomib treatment.

Contraception

Females

Advise females of reproductive potential to use effective contraception during treatment with bortezomib and for seven months after the last dose.

Males

Males with female partners of reproductive potential should use effective contraception during treatment with bortezomib and for four months after the last dose.

Infertility

Based on the mechanism of action and findings in animals, bortezomib may have an effect on either male or female fertility [see Nonclinical Toxicology (13.1)].

8.4 Pediatric Use

Safety and effectiveness of bortezomib have not been established in pediatric patients.

The activity and safety of bortezomib in combination with intensive reinduction chemotherapy was evaluated in pediatric and young adult patients with lymphoid malignancies (pre-B cell ALL 77%, 16% with T-cell ALL, and 7% T-cell lymphoblastic lymphoma (LL)), all of whom relapsed within 36 months of initial diagnosis in a single-arm multicenter, nonrandomized cooperative group trial. An effective reinduction multiagent chemotherapy regimen was administered in three blocks. Block 1 included vincristine, prednisone, doxorubicin and pegaspargase; Block 2 included cyclophosphamide, etoposide and methotrexate; Block 3 included high-dose cytosine arabinoside and asparaginase. bortezomib was administered at a dose of 1.3 mg/m^2 as a bolus intravenous injection on Days 1, 4, 8, and 11 of Block 1 and Days 1, 4, and 8 of Block 2. There were 140 patients with ALL or LL enrolled and evaluated for safety. The median age was ten years (range: 1 to 26), 57% were male, 70% were white, 14% were black, 4% were Asian, 2% were American Indian/Alaska Native, 1% were Pacific Islander.

The activity was evaluated in a prespecified subset of the first 60 evaluable patients enrolled on the study with pre-B ALL ≤ 21 years and relapsed < 36 months from diagnosis. The complete remission (CR) rate at day 36 was compared to that in a historical control set of patients who had received the identical backbone therapy without bortezomib. There was no evidence that the addition of bortezomib had any impact on the CR rate.

No new safety concerns were observed when bortezomib was added to a chemotherapy backbone regimen as compared with a historical control group in which the backbone regimen was given without bortezomib.

The BSA-normalized clearance of bortezomib in pediatric patients was similar to that observed in adults.

8.5 Geriatric Use

Of the 669 patients enrolled in the relapsed multiple myeloma study, 245 (37%) were 65 years of age or older: 125 (38%) on the bortezomib arm and 120 (36%) on the dexamethasone arm. Median time to progression and median duration of response for patients ≥ 65 were longer on bortezomib compared to dexamethasone [5.5 mo vs 4.3 mo, and 8.0 mo vs 4.9 mo, respectively]. On the bortezomib arm, 40% (n=46) of evaluable patients aged ≥ 65 experienced response (CR + PR) vs 18% (n=21) on the dexamethasone arm. The incidence of Grade 3 and 4 events was 64%, 78% and 75% for bortezomib patients ≤ 50, 51 to 64 and ≥ 65 years old, respectively [see Adverse Reactions (6.1), Clinical Studies (14.1)].

No overall differences in safety or effectiveness were observed between patients ≥ age 65 and younger patients receiving bortezomib; but greater sensitivity of some older individuals cannot be ruled out.

8.6 Renal Impairment

No starting dosage adjustment of bortezomib is recommended for patients with renal impairment. In patients requiring dialysis, bortezomib should be administered after the dialysis procedure [see Clinical Pharmacology (12.3)].

8.7 Hepatic Impairment

No starting dosage adjustment of bortezomib is recommended for patients with mild hepatic impairment (total bilirubin ≤ 1 × ULN and AST > ULN, or total bilirubin > 1 to 1.5 × ULN and any AST). The exposure of bortezomib is increased in patients with moderate (total bilirubin ≥ 1.5 to 3 × ULN and any AST) and severe (total bilirubin > 3 × ULN and any AST) hepatic impairment. Reduce the starting dose in patients with moderate or severe hepatic impairment [see Dosage and Administration (2.8), Clinical Pharmacology (12.3)].

8.8 Patients with Diabetes

During clinical trials, hypoglycemia and hyperglycemia were reported in diabetic patients receiving oral hypoglycemics. Patients on oral antidiabetic agents receiving bortezomib treatment may require close monitoring of their blood glucose levels and adjustment of the dose of their antidiabetic medication.

10 OVERDOSAGE

There is no known specific antidote for bortezomib overdosage. In humans, fatal outcomes following the administration of more than twice the recommended therapeutic dose have been reported, which were associated with the acute onset of symptomatic hypotension (5.2) and thrombocytopenia (5.7). In the event of an overdosage, the patient’s vital signs should be monitored and appropriate supportive care given.

Studies in monkeys and dogs showed that intravenous bortezomib doses as low as two times the recommended clinical dose on a mg/m^2 basis were associated with increases in heart rate, decreases in contractility, hypotension, and death. In dog studies, a slight increase in the corrected QT interval was observed at doses resulting in death. In monkeys, doses of 3 mg/m^2 and greater (approximately twice the recommended clinical dose) resulted in hypotension starting at one hour postadministration, with progression to death in 12 to 14 hours following drug administration.

11 DESCRIPTION

Bortezomib, a proteasome inhibitor, is an antineoplastic agent available for intravenous or subcutaneous injection. The chemical name for bortezomib {(1R)-3-Methyl-1-[(2S)-3-phenyl-2-(pyrazin-2-carboxamido)propanamido]butyl}boronic acid.

The structural formula is as follows:

The molecular formula of bortezomib is C19H25BN4O4; it has a molecular weight of 384.24. Bortezomib is freely soluble in methanol, ethanol and dimethyl sulfoxide, practically insoluble in toluene, pH range of 4 to 6.5.

BORUZU is available as a single-dose vial containing 3.5 mg of bortezomib as a sterile solution. Each 1 mL of solution contains 2.5 mg bortezomib, 25 mg mannitol, sodium chloride for isotonicity and water for injection.

12 CLINICAL PHARMACOLOGY

12.1 Mechanism of Action

Bortezomib is a reversible inhibitor of the chymotrypsin-like activity of the 26S proteasome in mammalian cells. The 26S proteasome is a large protein complex that degrades ubiquitinated proteins. The ubiquitin-proteasome pathway plays an essential role in regulating the intracellular concentration of specific proteins, thereby maintaining homeostasis within cells. Inhibition of the 26S proteasome prevents this targeted proteolysis, which can affect multiple signaling cascades within the cell. This disruption of normal homeostatic mechanisms can lead to cell death. Experiments have demonstrated that bortezomib is cytotoxic to a variety of cancer cell types in vitro. Bortezomib causes a delay in tumor growth in vivo in nonclinical tumor models, including multiple myeloma.

12.2 Pharmacodynamics

Following twice weekly administration of 1 mg/m^2 and 1.3 mg/m^2 bortezomib doses, the maximum inhibition of 20S proteasome activity (relative to baseline) in whole blood was observed five minutes after drug administration. Comparable maximum inhibition of 20S proteasome activity was observed between 1 and 1.3 mg/m^2 doses. Maximal inhibition ranged from 70% to 84% and from 73% to 83% for the 1 mg/m^2 and 1.3 mg/m^2 dose regimens, respectively.

12.3 Pharmacokinetics

Following intravenous administration of 1 mg/m^2 and 1.3 mg/m^2 doses, the mean maximum plasma concentrations of bortezomib (Cmax) after the first dose (Day 1) were 57 and 112 ng/mL, respectively. When administered twice weekly, the mean maximum observed plasma concentrations ranged from 67 to 106 ng/mL for the 1 mg/m^2 dose and 89 to 120 ng/mL for the 1.3 mg/m^2 dose.

Following an intravenous bolus or subcutaneous injection of a 1.3 mg/m^2 dose to patients with multiple myeloma, the total systemic exposure after repeat dose administration (AUClast) was equivalent for subcutaneous and intravenous administration. The AUClast geometric mean ratio (90% confidence interval) was 0.99 (0.80 to 1.23). The Cmax after subcutaneous administration (20.4 ng/mL) was lower than after intravenous administration (223 ng/mL) with repeat dose administration.

Distribution

The mean distribution volume of bortezomib ranged from approximately 498 to 1884 L/m^2 following single- or repeat-dose administration of 1 mg/m^2 or 1.3 mg/m^2 to patients with multiple myeloma. The binding of bortezomib to human plasma proteins averaged 83% over the concentration range of 100 to 1000 ng/mL.

Elimination

The mean elimination half-life of bortezomib upon multiple dosing ranged from 40 to 193 hours after the 1 mg/m^2 dose and 76 to 108 hours after the 1.3 mg/m^2 dose. The mean total body clearances were 102 and 112 L/h following the first dose for doses of 1 mg/m^2 and 1.3 mg/m^2, respectively, and ranged from 15 to 32 L/h following subsequent doses for doses of 1 and 1.3 mg/m^2, respectively.

Metabolism

Bortezomib is primarily oxidatively metabolized to several inactive metabolites in vitro via cytochrome P450 (CYP) enzymes 3A4, CYP2C19, and CYP1A2, and to a lesser extent by CYP2D6 and CYP2C9.

Excretion

The pathways of elimination of bortezomib have not been characterized in humans.

Specific Populations

No clinically significant differences in the pharmacokinetics of bortezomib were observed based on age, sex, or renal impairment (including patients administered bortezomib after dialysis). The effect of race on bortezomib pharmacokinetics is unknown.

Patients with Hepatic Impairment

Following administration of bortezomib doses ranging from 0.5 to 1.3 mg/m^2, mild (total bilirubin ≤ 1 × ULN and AST > ULN, or total bilirubin > 1 to 1.5 × ULN and any AST) hepatic impairment did not alter dose-normalized bortezomib AUC when compared to patients with normal hepatic function. Dose normalized mean bortezomib AUC increased by approximately 60% in patients with moderate (total bilirubin > 1.5 to 3 × ULN and any AST) or severe (total bilirubin > 3 × ULN and any AST) hepatic impairment. A lower starting dose is recommended in patients with moderate or severe hepatic impairment.

Drug Interaction Studies

Clinical Studies

No clinically significant differences in bortezomib pharmacokinetics were observed when coadministered with dexamethasone (weak CYP3A4 inducer), omeprazole (strong CYP2C19 inhibitor), or melphalan in combination with prednisone.

Strong CYP3A4 Inhibitor

Coadministration with ketoconazole (strong CYP3A4 inhibitor) increased bortezomib exposure by 35%.

Strong CYP3A4 Inducer

Coadministration with rifampin (strong CYP3A4 inducer) decreased bortezomib exposure by approximately 45%.

In Vitro Studies

Bortezomib may inhibit CYP2C19 activity and increase exposure to drugs that are substrates for this enzyme.

13 NONCLINICAL TOXICOLOGY

13.1 Carcinogenesis, Mutagenesis, Impairment of Fertility

Carcinogenicity studies have not been conducted with bortezomib.

Bortezomib showed clastogenic activity (structural chromosomal aberrations) in the in vitro chromosomal aberration assay using Chinese hamster ovary cells. Bortezomib was not genotoxic when tested in the in vitro mutagenicity assay (Ames test) and in vivo micronucleus assay in mice.

Fertility studies with bortezomib were not performed but evaluation of reproductive tissues has been performed in the general toxicity studies. In the six-month rat toxicity study, degenerative effects in the ovary were observed at doses ≥ 0.3 mg/m^2 (one-fourth of the recommended clinical dose), and degenerative changes in the testes occurred at 1.2 mg/m^2.

13.2 Animal Toxicology and/or Pharmacology

Cardiovascular Toxicity

Studies in monkeys showed that administration of dosages approximately twice the recommended clinical dose resulted in heart rate elevations, followed by profound progressive hypotension, bradycardia, and death 12 to 14 hours postdose. Doses ≥ 1.2 mg/m^2 induced dose-proportional changes in cardiac parameters. Bortezomib has been shown to distribute to most tissues in the body, including the myocardium. In a repeated dosing toxicity study in the monkey, myocardial hemorrhage, inflammation, and necrosis were also observed.

Chronic Administration

In animal studies at a dose and schedule similar to that recommended for patients (twice weekly dosing for two weeks followed by one week rest), toxicities observed included severe anemia and thrombocytopenia, and gastrointestinal, neurological and lymphoid system toxicities. Neurotoxic effects of bortezomib in animal studies included axonal swelling and degeneration in peripheral nerves, dorsal spinal roots, and tracts of the spinal cord. Additionally, multifocal hemorrhage and necrosis in the brain, eye, and heart were observed.

14 CLINICAL STUDIES

14.1 Multiple Myeloma

Randomized, Open-Label Clinical Study in Patients with Previously Untreated Multiple Myeloma

A prospective, international, randomized (1:1), open-label clinical study (NCT00111319) of 682 patients was conducted to determine whether bortezomib administered intravenously (1.3 mg/m^2) in combination with melphalan (9 mg/m^2) and prednisone (60 mg/m^2) resulted in improvement in time to progression (TTP) when compared to melphalan (9 mg/m^2) and prednisone (60 mg/m^2) in patients with previously untreated multiple myeloma. Treatment was administered for a maximum of nine cycles (approximately 54 weeks) and was discontinued early for disease progression or unacceptable toxicity. Antiviral prophylaxis was recommended for patients on the bortezomib study arm.

The median age of the patients in the study was 71 years (48;91), 50% were male, 88% were Caucasian and the median Karnofsky performance status score for the patients was 80 (60;100). Patients had IgG/IgA/Light chain myeloma in 63%/25%/8% instances, a median hemoglobin of 105 g/L (64;165), and a median platelet count of 221,500/microliter (33,000;587,000).

Efficacy results for the trial are presented in Table 14. At a prespecified interim analysis (with median follow-up of 16.3 months), the combination of bortezomib, melphalan and prednisone therapy resulted in significantly superior results for time to progression, progression-free survival, overall survival and response rate. Further enrollment was halted, and patients receiving melphalan and prednisone were offered bortezomib in addition. A later, prespecified analysis of overall survival (with median follow-up of 36.7 months with a hazard ratio of 0.65, 95% CI: 0.51, 0.84) resulted in a statistically significant survival benefit for the bortezomib, melphalan and prednisone treatment arm despite subsequent therapies including bortezomib based regimens. In an updated analysis of overall survival based on 387 deaths (median follow-up 60.1 months), the median overall survival for the bortezomib, melphalan and prednisone treatment arm was 56.4 months and for the melphalan and prednisone treatment arm was 43.1 months, with a hazard ratio of 0.695 (95% CI: 0.57, 0.85).

Table 14: Summary of Efficacy Analyses in the Previously Untreated Multiple Myeloma Study

Efficacy Endpoint | Bortezomib,; Melphalan and Prednisone; (n=344) | Melphalan and Prednisone; (n=338)
Time to Progression
Events n (%) | 101 (29) | 152 (45)
Median* (months); (95% CI) | 20.7; (17.6, 24.7) | 15.0; (14.1, 17.9)
Hazard ratio†; (95% CI) | 0.54; (0.42, 0.70)
p-value‡ | 0.000002
Progression-Free Survival
Events n (%) | 135 (39) | 190 (56)
Median* (months); (95% CI) | 18.3; (16.6, 21.7) | 14.0; (11.1, 15.0)
Hazard ratio†; (95% CI) | 0.61; (0.49, 0.76)
p-value‡ | 0.00001
Response Rate
CR§ n (%) | 102 (30) | 12 (4)
PR§ n (%) | 136 (40) | 103 (30)
nCR n (%) | 5 (1) | 0
CR + PR§ n (%) | 238 (69) | 115 (34)
p-value¶ | < 10^-10
Overall Survival at Median Follow-Up of 36.7 Months
Events (deaths) n (%) | 109 (32) | 148 (44)
Median* (months); (95% CI) | Not Reached; (46.2, NR) | 43.1; (34.8, NR)
Hazard ratio†; (95% CI) | 0.65; (0.51, 0.84)
p-value ‡ | 0.00084
Note: All results are based on the analysis performed at a median follow-up duration of 16.3 months except for the overall survival analysis.
* Kaplan-Meier estimate
† Hazard ratio estimate is based on a Cox proportional-hazard model adjusted for stratification factors: beta2-microglobulin, albumin, and region. A hazard ratio less than one indicates an advantage for bortezomib, melphalan and prednisone
‡ p-value based on the stratified log-rank test adjusted for stratification factors: beta2-microglobulin, albumin, and region
§ EBMT criteria
¶ p-value for Response Rate (CR + PR) from the Cochran-Mantel-Haenszel chi-square test adjusted for the stratification factors

TTP was statistically significantly longer on the bortezomib, melphalan and prednisone arm (see Figure 1). (median follow-up 16.3 months)

Figure 1: Time to Progression Bortezomib, Melphalan and Prednisone vs Melphalan and Prednisone

Overall survival was statistically significantly longer on the bortezomib, melphalan and prednisone arm (see Figure 2). (median follow-up 60.1 months)

Figure 2: Overall Survival Bortezomib, Melphalan and Prednisone vs Melphalan and Prednisone

Randomized, Clinical Study in Relapsed Multiple Myeloma of Bortezomib vs Dexamethasone

A prospective Phase 3, international, randomized (1:1), stratified, open-label clinical study (NCT00048230) enrolling 669 patients was designed to determine whether bortezomib resulted in improvement in time to progression (TTP) compared to high-dose dexamethasone in patients with progressive multiple myeloma following 1 to 3 prior therapies. Patients considered to be refractory to prior high-dose dexamethasone were excluded as were those with baseline Grade ≥ 2 peripheral neuropathy or platelet counts < 50,000/μL. A total of 627 patients were evaluable for response.

Stratification factors were based on the number of lines of prior therapy the patient had previously received (one previous line vs more than one line of therapy), time of progression relative to prior treatment (progression during or within six months of stopping their most recent therapy vs relapse > 6 months after receiving their most recent therapy), and screening beta2-microglobulin levels (≤ 2.5 mg/L vs > 2.5 mg/L).

Baseline patient and disease characteristics are summarized in Table 15.

Table 15: Summary of Baseline Patient and Disease Characteristics in the Relapsed Multiple Myeloma Study

Patient Characteristics | Bortezomib (N=333) | Dexamethasone (N=336)
Median age in years (range) | 62.0 (33, 84) | 61.0 (27, 86)
Gender: Male/female | 56%/44% | 60%/40%
Race: Caucasian/black/other | 90%/6%/4% | 88%/7%/5%
Karnofsky performance status score ≤ 70 | 13% | 17%
Hemoglobin < 100 g/L | 32% | 28%
Platelet count < 75 × 10^9/L | 6% | 4%
Disease Characteristics
Type of myeloma (%): IgG/IgA/Light chain | 60%/23%/12% | 59%/24%/13%
Median beta2-microglobulin (mg/L) | 3.7 | 3.6
Median albumin (g/L) | 39.0 | 39.0
Creatinine clearance ≤ 30 mL/min [n (%)] | 17 (5%) | 11 (3%)
Median Duration of Multiple Myeloma Since Diagnosis (Years) | 3.5 | 3.1
Number of Prior Therapeutic Lines of Treatment
Median | 2 | 2
1 prior line | 40% | 35%
> 1 prior line | 60% | 65%
Previous Therapy
Any prior steroids, e.g., dexamethasone, VAD | 98% | 99%
Any prior anthracyclines, e.g., VAD, mitoxantrone | 77% | 76%
Any prior alkylating agents, e.g., MP, VBMCP | 91% | 92%
Any prior thalidomide therapy | 48% | 50%
Vinca alkaloids | 74% | 72%
Prior stem cell transplant/other high-dose therapy | 67% | 68%
Prior experimental or other types of therapy | 3% | 2%

Patients in the bortezomib treatment group were to receive 8, three week treatment cycles followed by 3, five week treatment cycles of bortezomib. Patients achieving a CR were treated for four cycles beyond first evidence of CR. Within each three week treatment cycle, bortezomib 1.3 mg/m^2/dose alone was administered by intravenous bolus twice weekly for two weeks on Days 1, 4, 8, and 11 followed by a ten day rest period (Days 12 to 21). Within each five week treatment cycle, bortezomib 1.3 mg/m^2/dose alone was administered by intravenous bolus once weekly for four weeks on Days 1, 8, 15, and 22 followed by a 13 day rest period (Days 23 to 35) [see Dosage and Administration (2.2)].

Patients in the dexamethasone treatment group were to receive 4, five week treatment cycles followed by 5, four week treatment cycles. Within each five week treatment cycle, dexamethasone 40 mg/day PO was administered once daily on Days 1 to 4, 9 to 12, and 17 to 20 followed by a 15 day rest period (Days 21 to 35). Within each four week treatment cycle, dexamethasone 40 mg/day PO was administered once daily on Days 1 to 4 followed by a 24 day rest period (Days 5 to 28). Patients with documented progressive disease on dexamethasone were offered bortezomib at a standard dose and schedule on a companion study. Following a preplanned interim analysis of time to progression, the dexamethasone arm was halted and all patients randomized to dexamethasone were offered bortezomib, regardless of disease status.

In the bortezomib arm, 34% of patients received at least one bortezomib dose in all eight of the three week cycles of therapy, and 13% received at least one dose in all 11 cycles. The average number of bortezomib doses during the study was 22, with a range of 1 to 44. In the dexamethasone arm, 40% of patients received at least one dose in all four of the five week treatment cycles of therapy, and 6% received at least one dose in all nine cycles.

The time to event analyses and response rates from the relapsed multiple myeloma study are presented in Table 16. Response and progression were assessed using the European Group for Blood and Marrow Transplantation (EBMT) criteria. Complete response (CR) required < 5% plasma cells in the marrow, 100% reduction in M-protein, and a negative immunofixation test (IF^-). Partial response (PR) requires ≥ 50% reduction in serum myeloma protein and ≥ 90% reduction of urine myeloma protein on at least two occasions for a minimum of at least six weeks along with stable bone disease and normal calcium. Near complete response (nCR) was defined as meeting all the criteria for complete response including 100% reduction in M-protein by protein electrophoresis; however, M-protein was still detectable by immunofixation (IF^+).

Table 16: Summary of Efficacy Analyses in the Relapsed Multiple Myeloma Study

Efficacy Endpoint | All Patients |  | 1 Prior Line of Therapy |  | > 1 Prior Line of Therapy
Efficacy Endpoint | Bortezomib | Dex | Bortezomib | Dex | Bortezomib | Dex
Efficacy Endpoint | (n=333) | (n=336) | (n=132) | (n=119) | (n=200) | (n=217)
Time to Progression Events n (%) | 147 (44) | 196 (58) | 55 (42) | 64 (54) | 92 (46) | 132 (61)
Median* (95% CI) | 6.2 mo (4.9, 6.9) | 3.5 mo (2.9, 4.2) | 7.0 mo (6.2, 8.8) | 5.6 mo (3.4, 6.3) | 4.9 mo (4.2, 6.3) | 2.9 mo (2.8, 3.5)
Hazard ratio† (95% CI) | 0.55 (0.44, 0.69) |  | 0.55 (0.38, 0.81) |  | 0.54 (0.41, 0.72)
p-value‡ | < 0.0001 |  | 0.0019 |  | < 0.0001
Overall Survival Events (deaths) n (%) | 51 (15) | 84 (25) | 12 (9) | 24 (20) | 39 (20) | 60 (28)
Hazard ratio†; (95% Cl) | 0.57; (0.40, 0.81) |  | 0.39; (0.19, 0.81) |  | 0.65; (0.43, 0.97)
p-value‡, §§ | < 0.05 |  | < 0.05 |  | < 0.05
Response Rate; Population¶ n=627 | n=315 | n=312 | n=128 | n=110 | n=187 | n=202
CR# n (%) | 20 (6) | 2 (< 1) | 8 (6) | 2 (2) | 12 (6) | 0 (0)
PR# n (%) | 101 (32) | 54 (17) | 49 (38) | 27 (25) | 52 (28) | 27 (13)
nCR#, ♣ n (%) | 21 (7) | 3 (< 1) | 8 (6) | 2 (2) | 13 (7) | 1 (< 1)
CR + PR# n (%) | 121 (38) | 56 (18) | 57 (45) | 29 (26) | 64 (34) | 27 (13)
p-value♥ | < 0.0001 |  | 0.0035 |  | < 0.0001
* Kaplan-Meier estimate
† Hazard ratio is based on Cox proportional-hazard model with the treatment as single independent variable. A hazard ratio less than one indicates an advantage for bortezomib
‡ p-value based on the stratified log-rank test including randomization stratification factors
§§ Precise p-value cannot be rendered
¶ Response population includes patients who had measurable disease at baseline and received at least one dose of study drug
#EBMT criteria; nCR meets all EBMT criteria for CR but has positive IF. Under EBMT criteria nCR is in the PR category
♣ In two patients, the IF was unknown
♥ p-value for Response Rate (CR + PR) from the Cochran-Mantel-Haenszel chi-square test adjusted for the stratification factors

TTP was statistically significantly longer on the bortezomib arm (see Figure 3).

Figure 3: Time to Progression Bortezomib vs Dexamethasone (Relapsed Multiple Myeloma Study)

As shown in Figure 4, bortezomib had a significant survival advantage relative to dexamethasone (p < 0.05). The median follow-up was 8.3 months.

Figure 4: Overall Survival Bortezomib vs Dexamethasone (Relapsed Multiple Myeloma Study)

For the 121 patients achieving a response (CR or PR) on the bortezomib arm, the median duration was 8.0 months (95% CI: 6.9, 11.5 months) compared to 5.6 months (95% CI: 4.8, 9.2 months) for the 56 responders on the dexamethasone arm. The response rate was significantly higher on the bortezomib arm regardless of beta2-microglobulin levels at baseline.

Randomized, Open-Label Clinical Study of Bortezomib Subcutaneous vs Intravenous in Relapsed Multiple Myeloma

An open-label, randomized, Phase 3 noninferiority study (NCT00722566) compared the efficacy and safety of the subcutaneous administration of bortezomib vs the intravenous administration. This study included 222 bortezomib naïve patients with relapsed multiple myeloma, who were randomized in a 2:1 ratio to receive 1.3 mg/m^2 of bortezomib by either the subcutaneous (n=148) or intravenous (n=74) route for eight cycles. Patients who did not obtain an optimal response (less than Complete Response (CR)) to therapy with bortezomib alone after four cycles were allowed to receive oral dexamethasone 20 mg daily on the day of and after bortezomib administration (82 patients in subcutaneous treatment group and 39 patients in the intravenous treatment group). Patients with baseline Grade ≥ 2 peripheral neuropathy or neuropathic pain, or platelet counts < 50,000/µL were excluded. A total of 218 patients were evaluable for response.

Stratification factors were based on the number of lines of prior therapy the patient had received (one previous line vs more than one line of therapy), and international staging system (ISS) stage (incorporating beta2-microglobulin and albumin levels; Stages I, II, or III).

The baseline demographic and other characteristics of the two treatment groups are summarized as follows: the median age of the patient population was approximately 64 years of age (range: 38 to 88 years), primarily male (subcutaneous: 50%, intravenous: 64%); the primary type of myeloma is IgG (subcutaneous: 65% IgG, 26% IgA, 8% light chain; intravenous: 72% IgG, 19% IgA, 8% light chain), ISS staging I/II/III (%) was 27, 41, 32 for both subcutaneous and intravenous, Karnofsky performance status score was ≤ 70% in 22% of subcutaneous and 16% of intravenous, creatinine clearance was 67.5 mL/min in subcutaneous and 73 mL/min in intravenous, the median years from diagnosis was 2.68 and 2.93 in subcutaneous and intravenous respectively and the proportion of patients with more than one prior line of therapy was 38% in subcutaneous and 35% in intravenous.

This study met its primary (noninferiority) objective that single agent subcutaneous bortezomib retains at least 60% of the overall response rate after four cycles relative to single agent intravenous bortezomib. The results are provided in Table 17.

Table 17: Summary of Efficacy Analyses in the Relapsed Multiple Myeloma Study of Bortezomib Subcutaneous vs Intravenous

 | Subcutaneous Bortezomib | Intravenous Bortezomib
Intent to Treat Population | (n=148) | (n=74)
Primary Endpoint
Response Rate at 4 Cycles
ORR (CR + PR) n(%) | 63 (43) | 31 (42)
Ratio of Response Rates (95% CI) | 1.01 (0.73, 1.40)
CR n (%) | 11 (7) | 6 (8)
PR n (%) | 52 (35) | 25 (34)
nCR n (%) | 9 (6) | 4 (5)
Secondary Endpoints
Response Rate at 8 Cycles
ORR (CR + PR) | 78 (53) | 38 (51)
CR n (%) | 17 (11) | 9 (12)
PR n (%) | 61 (41) | 29 (39)
nCR n (%) | 14 (9) | 7 (9)
Median Time to Progression, months | 10.4 | 9.4
Median Progression-Free Survival, months | 10.2 | 8.0
1 Year Overall Survival (%)* | 72.6 | 76.7
* Median duration of follow-up is 11.8 months

A Randomized, Phase 2 Dose-Response Study in Relapsed Multiple Myeloma

An open-label, multicenter study randomized 54 patients with multiple myeloma who had progressed or relapsed on or after front-line therapy to receive bortezomib 1 mg/m^2 or 1.3 mg/m^2 intravenous bolus twice weekly for two weeks on Days 1, 4, 8, and 11 followed by a ten day rest period (Days 12 to 21). The median duration of time between diagnosis of multiple myeloma and first dose of bortezomib on this trial was two years, and patients had received a median of one prior line of treatment (median of three prior therapies). A single complete response was seen at each dose. The overall response rates (CR + PR) were 30% (8/27) at 1 mg/m^2 and 38% (10/26) at 1.3 mg/m^2.

A Phase 2 Open-Label Extension Study in Relapsed Multiple Myeloma

Patients from the two Phase 2 studies, who in the investigators’ opinion would experience additional clinical benefit, continued to receive bortezomib beyond 8 cycles on an extension study. Sixty-three (63) patients from the Phase 2 multiple myeloma studies were enrolled and received a median of seven additional cycles of bortezomib therapy for a total median of 14 cycles (range: 7 to 32). The overall median dosing intensity was the same in both the parent protocol and extension study. Sixty-seven percent (67%) of patients initiated the extension study at the same or higher dose intensity at which they completed the parent protocol, and 89% of patients maintained the standard three week dosing schedule during the extension study. No new cumulative or new long-term toxicities were observed with prolonged bortezomib treatment [see Adverse Reactions (6.1)].

A Single-Arm Trial of Retreatment in Relapsed Multiple Myeloma

A single-arm, open-label trial (NCT00431769) was conducted to determine the efficacy and safety of retreatment with bortezomib. One hundred and thirty patients (≥ 18 years of age) with multiple myeloma who previously had at least partial response on a bortezomib-containing regimen (median of two prior lines of therapy [range: 1 to 7]) were retreated upon progression with bortezomib administered intravenously. Patients were excluded from trial participation if they had peripheral neuropathy or neuropathic pain of Grade ≥ 2. At least six months after prior bortezomib therapy, bortezomib was restarted at the last tolerated dose of 1.3 mg/m^2 (n=93) or ≤ 1 mg/m^2 (n=37) and given on Days 1, 4, 8 and 11 every three weeks for maximum of eight cycles either as single agent or in combination with dexamethasone in accordance with the standard of care. Dexamethasone was administered in combination with bortezomib to 83 patients in Cycle 1 with an additional 11 patients receiving dexamethasone during the course of bortezomib retreatment cycles.

The primary endpoint was best confirmed response to retreatment as assessed by European Group for Blood and Marrow Transplantation (EBMT) criteria. Fifty of the 130 patients achieved a best confirmed response of Partial Response or better for an overall response rate of 38.5% (95% CI: 30.1, 47.4). One patient achieved a Complete Response and 49 achieved Partial Response. In the 50 responding patients, the median duration of response was 6.5 months and the range was 0.6 to 19.3 months.

14.2 Mantle Cell Lymphoma

A Randomized, Open-Label Clinical Study in Patients with Previously Untreated Mantle Cell Lymphoma

A randomized, open-label, Phase 3 study (NCT00722137) was conducted in 487 adult patients with previously untreated mantle cell lymphoma (Stage II, III or IV) who were ineligible or not considered for bone marrow transplantation to determine whether bortezomib administered in combination with rituximab, cyclophosphamide, doxorubicin, and prednisone (BR-CAP) resulted in improvement in progression-free survival (PFS) when compared to the combination of rituximab, cyclophosphamide, doxorubicin, vincristine, and prednisone (R-CHOP). This clinical study utilized independent pathology confirmation and independent radiologic response assessment.

Patients in the BR-CAP treatment arm received bortezomib (1.3 mg/m^2) administered intravenously on Days 1, 4, 8, and 11 (rest period Days 12 to 21); rituximab (375 mg/m^2) on Day 1; cyclophosphamide (750 mg/m^2) on Day 1; doxorubicin (50 mg/m^2) on Day 1; and prednisone (100 mg/m^2) on Day 1 through Day 5 of the 21 day treatment cycle. For patients with a response first documented at Cycle 6, two additional treatment cycles were allowed.

Median patient age was 66 years, 74% were male, 66% were Caucasian and 32% were Asian. Sixty-nine percent of patients had a positive bone marrow aspirate and/or a positive bone marrow biopsy for MCL, 54% of patients had an International Prognostic Index (IPI) score of three (highintermediate) or higher and 76% had Stage IV disease.

The majority of the patients in both groups received six or more cycles of treatment, 84% in the BR-CAP group and 83% in the R-CHOP group. Median number of cycles received by patients in both treatment arms was six with 17% of patients in the R-CHOP group and 14% of subjects in the BR-CAP group receiving up to two additional cycles.

The efficacy results for PFS, CR and ORR with a median follow-up of 40 months are presented in Table 18. The response criteria used to assess efficacy were based on the International Workshop to Standardize Response Criteria for Non-Hodgkin’s Lymphoma (IWRC). Final overall survival results at a median follow-up of 78.5 months are also presented in Table 18 and Figure 6. The combination of BR-CAP resulted in statistically significant prolongation of PFS compared with R-CHOP (see Table 18, Figure 5).

Table 18: Summary of Efficacy Analyses in the Previously Untreated Mantle Cell Lymphoma Study

Efficacy Endpoint n: Intent to Treat patients | BR-CAP (n=243) | R-CHOP (n=244)
Progression-Free Survival (by independent radiographic assessment)
Events n (%) | 133 (55) | 165 (68)
Median* (months); (95% CI) | 25; (20, 32) | 14; (12, 17)
Hazard ratio†; (95% CI) | 0.63; (0.50, 0.79)
p-value‡ | < 0.001
Complete Response Rate (CR)§
n (%); (95% CI) | 108 (44); (38, 51) | 82 (34); (28, 40)
Overall Response Rate (CR + Cru + PR)¶
n (%) | 214 (88) | 208 (85)
(95% CI) | (83, 92) | (80, 89)
Overall Survival
Events n (%) | 103 (42) | 138 (57)
Median* (months); (95% CI) | 91; (71, NE) | 56; (47, 69)
Hazard Ratio†; (95% CI) | 0.66; (0.51, 0.85)
Note: All results are based on the analysis performed at a median follow-up duration of 40 months except for the overall survival analysis, which was performed at a median follow-up of 78.5 months.
CI = Confidence Interval; IPI = International Prognostic Index; LDH = Lactate dehydrogenase
* Based on Kaplan-Meier product limit estimates.
† Hazard ratio estimate is based on a Cox’s model stratified by IPI risk and stage of disease. A hazard ratio < 1 indicates an advantage for BR-CAP.
‡ Based on Log rank test stratified with IPI risk and stage of disease.
§ Includes CR by independent radiographic assessment, bone marrow, and LDH using ITT population.
¶ Includes CR + Cru + PR by independent radiographic assessment, regardless of the verification by bone marrow and LDH, using ITT population.

Figure 5: Progression-Free Survival BR-CAP vs R-CHOP (previously Untreated Mantle Cell Lymphoma Study)

Key: R-CHOP = rituximab, cyclophosphamide, doxorubicin, vincristine, and prednisone; BR-CAP = bortezomib, rituximab, cyclophosphamide, doxorubicin, and prednisone.

Figure 6: Overall Survival BR-CAP vs R-CHOP (previously Untreated Mantle Cell Lymphoma Study)

Key: R-CHOP = rituximab, cyclophosphamide, doxorubicin, vincristine, and prednisone; BR-CAP = bortezomib, rituximab, cyclophosphamide, doxorubicin, and prednisone.

A Phase 2 Single-Arm Clinical Study in Relapsed Mantle Cell Lymphoma after Prior Therapy

The safety and efficacy of bortezomib in relapsed or refractory mantle cell lymphoma were evaluated in an open-label, single-arm, multicenter study (NCT00063713) of 155 patients with progressive disease who had received at least one prior therapy. The median age of the patients was 65 years (42, 89), 81% were male, and 92% were Caucasian. Of the total, 75% had one or more extra-nodal sites of disease, and 77% were Stage 4. In 91% of the patients, prior therapy included all of the following: an anthracycline or mitoxantrone, cyclophosphamide, and rituximab. A total of thirty-seven percent (37%) of patients were refractory to their last prior therapy. An intravenous bolus injection of bortezomib 1.3 mg/m^2/dose was administered twice weekly for two weeks on Days 1, 4, 8, and 11 followed by a ten day rest period (Days 12 to 21) for a maximum of 17 treatment cycles. Patients achieving a CR or CRu were treated for four cycles beyond first evidence of CR or CRu. The study employed dose modifications for toxicity [see Dosage and Administration (2.6, 2.7)].

Responses to bortezomib are shown in Table 19. Response rates to bortezomib were determined according to the International Workshop Response Criteria (IWRC) based on independent radiologic review of CT scans. The median number of cycles administered across all patients was four; in responding patients the median number of cycles was eight. The median time to response was 40 days (range: 31 to 204 days). The median duration of follow-up was more than 13 months.

Table 19: Response Outcomes in a Phase 2 Relapsed Mantle Cell Lymphoma Study

Response Analyses (N=155) | N (%) | 95% CI
Overall Response Rate (IWRC) (CR + CRu + PR) | 48 (31) | (24, 39)
Complete Response (CR + CRu) | 12 (8) | (4, 13)
CR | 10 (6) | (3, 12)
CRu | 2 (1) | (0, 5)
Partial Response (PR) | 36 (23) | (17, 31)
Duration of Response | Median | 95% CI
CR + CRu + PR (N=48) | 9.3 months | (5.4, 13.8)
CR + CRu (N=12) | 15.4 months | (13.4, 15.4)
PR (N=36) | 6.1 months | (4.2, 9.3)

15 REFERENCES

1. “OSHA Hazardous Drugs” (refer to antineoplastic weblinks including OSHA Technical Manual) OSHA. http://www.osha.gov/SLTC/hazardousdrugs/index.html

16 HOW SUPPLIED/STORAGE AND HANDLING

BORUZU® (bortezomib injection) is a sterile clear to light yellow solution supplied as a carton containing one single-dose vial.

BORUZU® (bortezomib injection), 3.5 mg/1.4 mL (2.5 mg/mL); NDC 70121-2484-1

Store refrigerated at 2°C to 8°C (36°F to 46°F) in original package to protect from light.

Follow guidelines for handling and disposal for hazardous drugs, including the use of gloves and other protective clothing to prevent skin contact^1.

17 PATIENT COUNSELING INFORMATION

Discuss the following with patients prior to treatment with BORUZU:

Peripheral Neuropathy

Advise patients to report the development or worsening of sensory and motor peripheral neuropathy to their healthcare provider [see Warnings and Precautions (5.1)].

Hypotension

Advise patients to drink adequate fluids to avoid dehydration and to report symptoms of hypotension to their healthcare provider [see Warnings and Precautions (5.2)].

Instruct patients to seek medical advice if they experience symptoms of dizziness, light headedness or fainting spells, or muscle cramps.

Cardiac Toxicity

Advise patients to report signs or symptoms of heart failure to their healthcare provider [see Warnings and Precautions (5.3)].

Pulmonary Toxicity

Advise patients to report symptoms of ARDS, pulmonary hypertension, pneumonitis, and pneumonia immediately to their healthcare provider [see Warnings and Precautions (5.4)].

Posterior Reversible Encephalopathy Syndrome (PRES)

Advise patients to seek immediate medical attention for signs or symptoms of PRES [see Warnings and Precautions (5.5)].

Gastrointestinal Toxicity

Advise patients to report symptoms of gastrointestinal toxicity to their healthcare provider and to drink adequate fluids to avoid dehydration. Instruct patients to seek medical advice if they experience symptoms of dizziness, light headedness or fainting spells, or muscle cramps [see Warnings and Precautions (5.6)].

Thrombocytopenia/Neutropenia

Advise patients to report signs or symptoms of bleeding or infection immediately to their healthcare provider [see Warnings and Precautions (5.7)].

Tumor Lysis Syndrome

Advise patients of the risk of tumor lysis syndrome and to drink adequate fluids to avoid dehydration

[see Warnings and Precautions (5.8)].

Hepatic Toxicity

Advise patients to report signs or symptoms of hepatic toxicity to their healthcare provider [see Warnings and Precautions (5.9)].

Thrombotic Microangiopathy

Advise patients to seek immediate medical attention if any signs or symptoms of thrombotic microangiopathy occur [see Warnings and Precautions (5.10)].

Ability to Drive or Operate Machinery or Impairment of Mental Ability

BORUZU may cause fatigue, dizziness, syncope, orthostatic/postural hypotension. Advise patients not to drive or operate machinery if they experience any of these symptoms [see Warnings and Precautions (5.2, 5.5)].

Embryo-Fetal Toxicity

Advise females of the potential risk to the fetus and to use effective contraception during treatment with BORUZU and for seven months following the last dose. Advise male patients with female partners of reproductive potential to use effective contraception during treatment with BORUZU and for four months following the last dose. Instruct patients to report pregnancy to their physicians immediately if they or their female partner becomes pregnant during treatment or within seven months following last dose [see Warnings and Precautions (5.11)].

Lactation

Advise women not to breastfeed while receiving BORUZU and for two months after last dose [see Use in Specific Populations (8.2)].

Concomitant Medications

Advise patients to speak with their physicians about any other medication they are currently taking.

Diabetic Patients

Advise patients to check their blood sugar frequently if using an oral antidiabetic medication and to notify their physicians of any changes in blood sugar level.

Dermal

Advise patients to contact their physicians if they experience rash, severe injection site reactions [see Dosage and Administration (2.9)], or skin pain. Discuss with patients the option for antiviral prophylaxis for herpes virus infection [see Adverse Reactions (6.1)].

Other

Instruct patients to contact their physicians if they develop an increase in blood pressure, bleeding, fever, constipation, or decreased appetite.

Manufactured by:

Amneal Oncology Pvt. Ltd.

Telangana 509301, INDIA

Distributed by:

Amneal Pharmaceuticals LLC

Bridgewater, NJ 08807

Rev. 07-2025-01

PACKAGE LABEL.PRINCIPAL DISPLAY PANEL

NDC 70121-2484-1

BORUZU® (bortezomib injection)

3.5 mg/1.4 mL (2.5 mg/mL)

For Intravenous or Subcutaneous use

Rx only

Vial Label

Amneal Pharmaceuticals LLC

NDC 70121-2484-1

BORUZU® (bortezomib injection)

3.5 mg/1.4 mL (2.5 mg/mL)

For Intravenous or Subcutaneous use

Rx only

Carton - Front Side

Amneal Pharmaceuticals LLC

NDC 70121-2484-1

BORUZU® (bortezomib injection)

3.5 mg/1.4 mL (2.5 mg/mL)

For Intravenous or Subcutaneous use

Rx only

Carton Label - Inner Side

Amneal Pharmaceuticals LLC

BORUZU® (bortezomib injection)

3.5 mg/1.4 mL (2.5 mg/mL)

For Intravenous or Subcutaneous use

Rx only

Sticker Label

Amneal Pharmaceuticals LLC